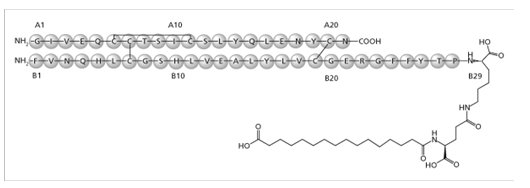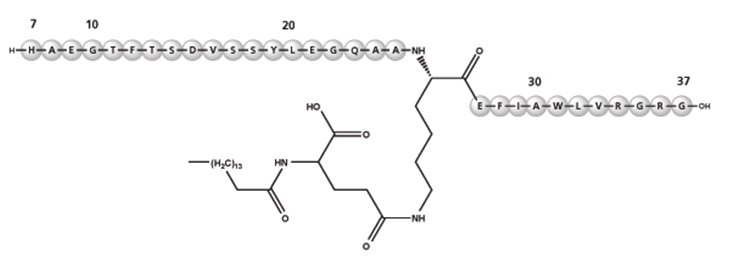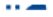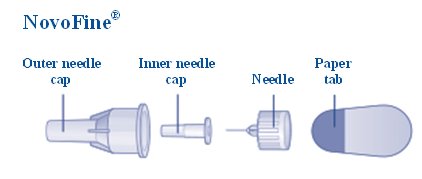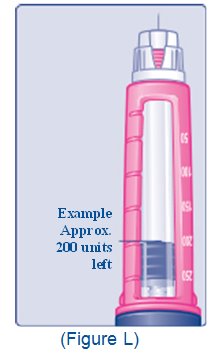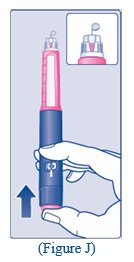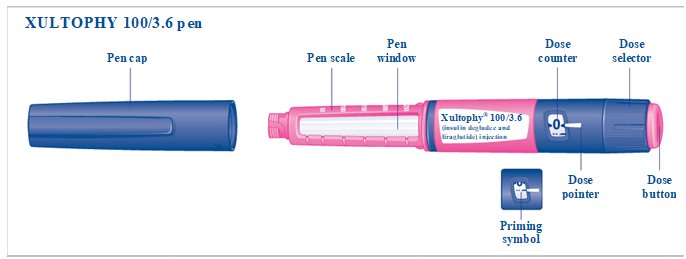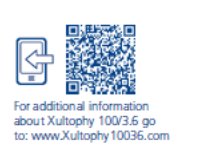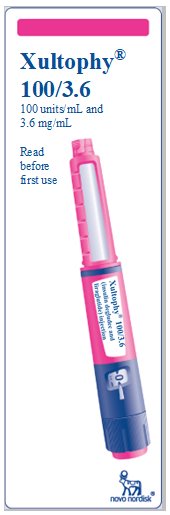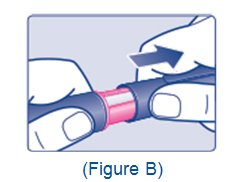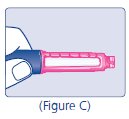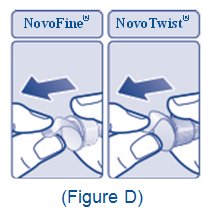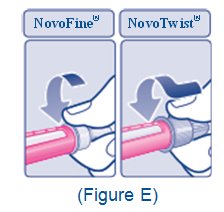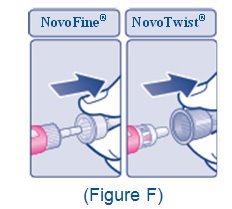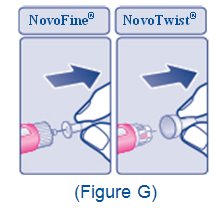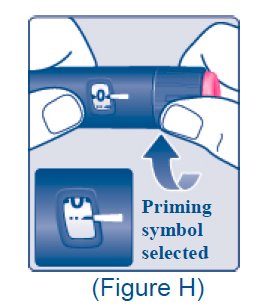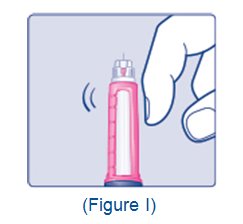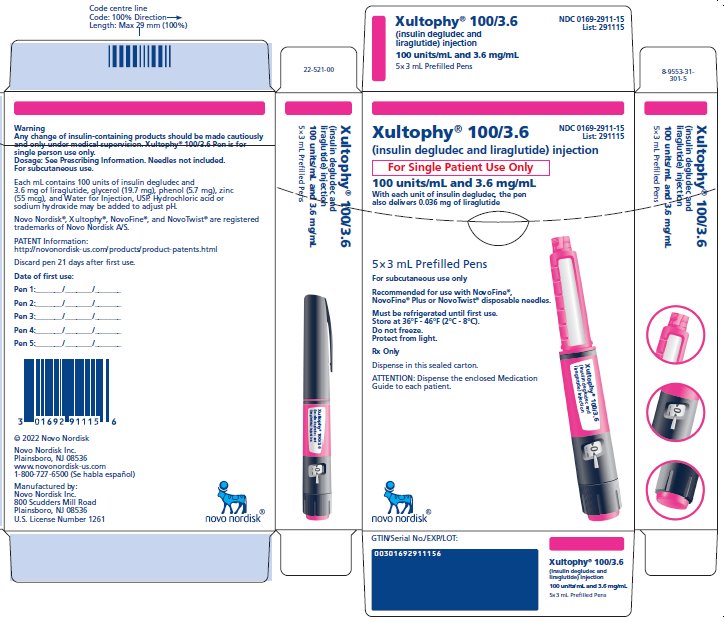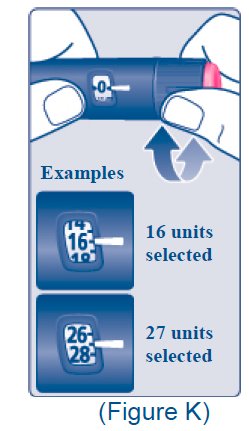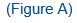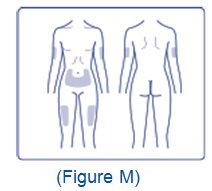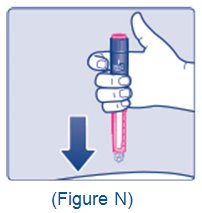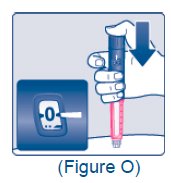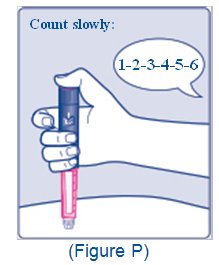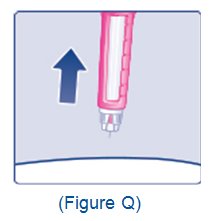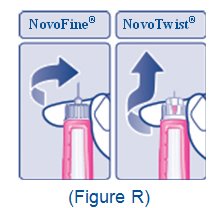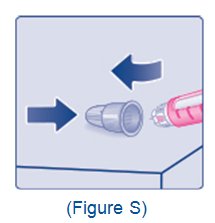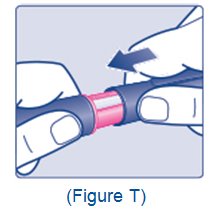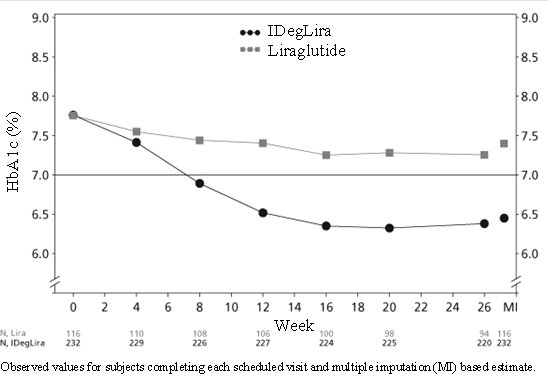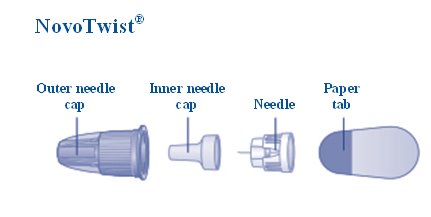 DRUG LABEL: Xultophy 100/3.6
NDC: 0169-2911 | Form: INJECTION, SOLUTION
Manufacturer: Novo Nordisk
Category: prescription | Type: HUMAN PRESCRIPTION DRUG LABEL
Date: 20251014

ACTIVE INGREDIENTS: INSULIN DEGLUDEC 100 [iU]/1 mL; LIRAGLUTIDE 3.6 mg/1 mL
INACTIVE INGREDIENTS: GLYCERIN 19.7 mg/1 mL; PHENOL 5.70 mg/1 mL; ZINC 55 ug/1 mL; WATER

HIGHLIGHTS OF PRESCRIBING INFORMATION

These highlights do not include all the information needed to use XULTOPHY 100/3.6 safely and effectively. See full prescribing information for XULTOPHY 100/3.6.
XULTOPHY® 100/3.6 (insulin degludec and liraglutide) injection, for subcutaneous use
Initial U.S. Approval: 2016

RECENT MAJOR CHANGES

Warnings and Precautions,

Severe Gastrointestinal Adverse Reactions (5.8) …………. 10/2025
Pulmonary Aspiration During General Anesthesia or Deep
  Sedation (5.13) ……………..…………………….…… 11/2024

WARNING: RISK OF THYROID C-CELL TUMORS

See full prescribing information for complete boxed warning.

- Liraglutide, one of the components of XULTOPHY 100/3.6, causes thyroid C-cell tumors at clinically relevant exposures in both genders of rats and mice. It is unknown whether XULTOPHY 100/3.6 causes thyroid C-cell tumors, including medullary thyroid carcinoma (MTC), in humans, as the human relevance of liraglutide-induced rodent thyroid C-cell tumors has not been determined. (5.1, 13.1)
- XULTOPHY 100/3.6 is contraindicated in patients with a personal or family history of MTC or in patients with Multiple Endocrine Neoplasia syndrome type 2 (MEN 2). Counsel patients regarding the potential risk of MTC and the symptoms of thyroid tumors. (4, 5.1)

1 INDICATIONS AND USAGE

XULTOPHY 100/3.6 is a combination of insulin degludec, a long-acting human insulin analog, and liraglutide, a glucagon-like peptide-1 (GLP-1) receptor agonist, indicated as an adjunct to diet and exercise to improve glycemic control in adults with type 2 diabetes mellitus.

Limitations of Use: (1)

- Coadministration with any other product containing liraglutide or another GLP-1 receptor agonist is not recommended.
- Not recommended for the treatment of diabetic ketoacidosis.
- Has not been studied in combination with prandial insulin.

2 DOSAGE AND ADMINISTRATION

- Administer once-daily at same time each day with or without food. (2.1)
- XULTOPHY 100/3.6 pen delivers doses from 10 to 50 units with each injection (2.1, 2.2); each XULTOPHY 100/3.6 dosage unit contains 1 unit of insulin degludec and 0.036 mg of liraglutide. (2.1)
- Maximum daily dosage is 50 units (50 units of insulin degludec and 1.8 mg of liraglutide). (2.1)
- Recommended starting dosage in patients naïve to basal insulin or GLP-1 receptor agonist is 10 units (10 units of insulin degludec and 0.36 mg of liraglutide) injected subcutaneously once-daily. (2.2)
- Discontinue therapy with liraglutide or basal insulin prior to initiation of XULTOPHY 100/3.6. (2.2)
- Recommended starting dosage in patients currently on basal insulin or GLP-1 receptor agonist is 16 units (16 units of insulin degludec and 0.58 mg of liraglutide) injected subcutaneously once-daily. (2.2)
- See Full Prescribing Information for titration recommendations. (2.3)
- Inject XULTOPHY 100/3.6 subcutaneously into the thigh, upper arm, or abdomen. (2.5)
- Rotate injection sites to reduce risk of lipodystrophy and localized cutaneous amyloidosis. (2.5)
- Do not administer intravenously or by an infusion pump. (2.5)
- Do not dilute or mix with any other insulin products or solutions. (2.5)

3 DOSAGE FORMS AND STRENGTHS

Injection: 100 units/mL of insulin degludec and 3.6 mg/mL of liraglutide available in:

- 3 mL single-patient-use pen. (3)

4 CONTRAINDICATIONS

- Patients with a personal or family history of medullary thyroid carcinoma or in patients with Multiple Endocrine Neoplasia syndrome type 2 (4)
- During episodes of hypoglycemia (4)
- Patients with a serious hypersensitivity reaction to insulin degludec, liraglutide, or any of the excipients in XULTOPHY 100/3.6 (4)

5 WARNINGS AND PRECAUTIONS

- Acute Pancreatitis: Has been observed in patients treated with GLP-1 receptor agonists, including liraglutide. Discontinue if pancreatitis is suspected. (5.2)
- Never share a XULTOPHY 100/3.6 pen between patients, even if the needle is changed. (5.3)
- Hyperglycemia or hypoglycemia with changes in insulin regimen: Make changes to a patient’s insulin regimen (e.g., insulin strength, manufacturer, type, injection site or method of administration) under close medical supervision with increased frequency of blood glucose monitoring. (5.4)
- Overdose due to medication errors: XULTOPHY 100/3.6 contains two drugs. Instruct patients to check label before injection since accidental mix-ups with insulin containing products can occur. Do not exceed the maximum dose or administer with other GLP-1 receptor agonists. (5.5)
- Hypoglycemia: May be life-threatening. Increase monitoring with changes to: dosage, concomitant drugs, meal pattern, physical activity; and in patients with renal impairment or hepatic impairment or hypoglycemia unawareness. (5.6)
- Acute Kidney Injury Due to Volume Depletion: Monitor renal function in patients reporting adverse reactions that could lead to volume depletion. (5.7)
- Severe Gastrointestinal Adverse Reactions: Use has been associated with gastrointestinal adverse reactions, sometimes severe. XULTOPHY 100/3.6 is not recommended in patients with severe gastroparesis. (5.8)
- Hypersensitivity Reactions: Severe, life-threatening, generalized allergy, including anaphylaxis, angioedema, bronchospasm, hypotension, and shock can occur. If a hypersensitivity reaction occurs, discontinue and treat per standard of care. (5.9)
- Acute Gallbladder Disease: If cholelithiasis or cholecystitis are suspected, gallbladder studies are indicated. (5.10)
- Hypokalemia: May be life-threatening. Monitor potassium levels in patients at risk for hypokalemia and treat if indicated. (5.11)
- Fluid retention and congestive heart failure with use of thiazolidinediones (TZDs): Observe for signs and symptoms of heart failure; consider dosage reduction or discontinuation if heart failure occurs. (5.12)
- Pulmonary Aspiration During General Anesthesia or Deep Sedation: Has been reported in patients receiving GLP-1 receptor agonists undergoing elective surgeries or procedures. Instruct patients to inform healthcare providers of any planned surgeries or procedures. (5.13)

6 ADVERSE REACTIONS

- Most common adverse reactions (incidence ≥5%) in clinical trials are nasopharyngitis, headache, nausea, diarrhea, increased lipase and upper respiratory tract infection. (6)
- Immunogenicity-related events, including urticaria, were more common among liraglutide-treated patients (0.8%) than among comparator-treated patients (0.4%) in clinical trials. (12.6)

To report SUSPECTED ADVERSE REACTIONS, contact Novo Nordisk Inc. at 1-800-727-6500 or FDA at 1-800-FDA-1088 or www.fda.gov/medwatch.

7 DRUG INTERACTIONS

- Drugs that affect glucose metabolism: Adjustment of XULTOPHY 100/3.6 dosage may be needed; closely monitor blood glucose. (7.1)
- Anti-Adrenergic drugs (e.g., beta-blockers, clonidine, guanethidine, and reserpine): Hypoglycemia signs and symptoms may be reduced or absent. (7.1)
- Effects of delayed gastric emptying on oral medications: May impact absorption of concomitantly administered oral medications. (7.2)

8 USE IN SPECIFIC POPULATIONS

Pregnancy: XULTOPHY 100/3.6 should be used during pregnancy only if the potential benefit justifies the potential risk to the fetus. (8.1)

FULL PRESCRIBING INFORMATION

WARNING: RISK OF THYROID C-CELL TUMORS

- Liraglutide, one of the components of XULTOPHY 100/3.6, causes dose-dependent and treatment-duration-dependent thyroid C-cell tumors at clinically relevant exposures in both genders of rats and mice. It is unknown whether XULTOPHY 100/3.6 causes thyroid C-cell tumors, including medullary thyroid carcinoma (MTC), in humans, as the human relevance of liraglutide-induced rodent thyroid C-cell tumors has not been determined [see Warnings and Precautions (5.1), Nonclinical Toxicology (13)].
- XULTOPHY 100/3.6 is contraindicated in patients with a personal or family history of MTC and in patients with Multiple Endocrine Neoplasia syndrome type 2 (MEN 2). Counsel patients regarding the potential risk for MTC with the use of XULTOPHY 100/3.6 and inform them of symptoms of thyroid tumors (e.g., a mass in the neck, dysphagia, dyspnea, persistent hoarseness). Routine monitoring of serum calcitonin or using thyroid ultrasound is of uncertain value for early detection of MTC in patients treated with XULTOPHY 100/3.6 [see Contraindications (4), Warnings and Precautions (5.1)].

1 INDICATIONS AND USAGE

XULTOPHY 100/3.6 is a combination of insulin degludec and liraglutide and is indicated as an adjunct to diet and exercise to improve glycemic control in adults with type 2 diabetes mellitus.

Limitations of Use:

- XULTOPHY 100/3.6 contains liraglutide. Coadministration with any other product containing liraglutide or another glucagon-like peptide-1 (GLP-1) receptor agonist is not recommended [see Warnings and Precautions (5.5)].
- XULTOPHY 100/3.6 is not recommended for the treatment of diabetic ketoacidosis.
- XULTOPHY 100/3.6 has not been studied in combination with prandial insulin.

2 DOSAGE AND ADMINISTRATION

2.1 Important Dosage Information

- XULTOPHY 100/3.6 is a combination of insulin degludec and liraglutide.
- Administer XULTOPHY 100/3.6 by subcutaneous injection once-daily at the same time each day with or without food.
- The XULTOPHY 100/3.6 pen delivers doses from 10 to 50 units with each injection. Table 1 presents the units of insulin degludec and the milligrams of liraglutide in each dosage of XULTOPHY 100/3.6 [see Dosage and Administration (2.2)].
- The maximum dosage of XULTOPHY 100/3.6 is 50 units daily (50 units of insulin degludec and 1.8 mg of liraglutide) [see Warnings and Precautions (5.5)].

2.2 Recommended Starting Dosage

In patients naïve to basal insulin or a GLP-1 receptor agonist

- The recommended starting dosage of XULTOPHY 100/3.6 is 10 units (10 units of insulin degludec and 0.36 mg of liraglutide) injected subcutaneously once-daily (see Table 1).

In patients currently on basal insulin or a GLP-1 receptor agonist

- Discontinue therapy with basal insulin or GLP-1 receptor agonist prior to initiation of XULTOPHY 100/3.6.
- The recommended starting dosage of XULTOPHY 100/3.6 is 16 units (16 units of insulin degludec and 0.58 mg of liraglutide) injected subcutaneously once-daily (see Table 1).

Table 1. Units of Insulin Degludec and Milligrams of Liraglutide in Each Dosage of XULTOPHY 100/3.6

XULTOPHY 100/3.6; (dose counter display)* | insulin degludec; component dose | liraglutide; component dose | Comment
▪▪ ─ | --- | --- | Priming symbol
10 | 10 units | 0.36 mg | Recommended starting dose for patients naïve to basal insulin or GLP-1 receptor agonist
11 | 11 units | 0.4 mg
12 | 12 units | 0.43 mg
13 | 13 units | 0.47 mg
14 | 14 units | 0.5 mg
15 | 15 units | 0.54 mg
16 | 16 units | 0.58 mg | Recommended starting dose for patients currently on basal insulin or GLP-1 receptor agonist
17 | 17 units | 0.61 mg
18 | 18 units | 0.65 mg
19 | 19 units | 0.68 mg
20 | 20 units | 0.72 mg
21 | 21 units | 0.76 mg
22 | 22 units | 0.79 mg
23 | 23 units | 0.83 mg
24 | 24 units | 0.86 mg
25 | 25 units | 0.9 mg
26 | 26 units | 0.94 mg
27 | 27 units | 0.97 mg
28 | 28 units | 1.01 mg
29 | 29 units | 1.04 mg
30 | 30 units | 1.08 mg
31 | 31 units | 1.12 mg
32 | 32 units | 1.15 mg
33 | 33 units | 1.19 mg
34 | 34 units | 1.22 mg
35 | 35 units | 1.26 mg
36 | 36 units | 1.3 mg
37 | 37 units | 1.33 mg
38 | 38 units | 1.37 mg
39 | 39 units | 1.4 mg
40 | 40 units | 1.44 mg
41 | 41 units | 1.48 mg
42 | 42 units | 1.51 mg
43 | 43 units | 1.55 mg
44 | 44 units | 1.58 mg
45 | 45 units | 1.62 mg
46 | 46 units | 1.66 mg
47 | 47 units | 1.69 mg
48 | 48 units | 1.73 mg
49 | 49 units | 1.76 mg
50 | 50 units | 1.8 mg | Maximum daily dosage [see Warnings and Precautions (5.5)]

*The dose counter on the XULTOPHY 100/3.6 pen displays numbers for the even units and displays lines for the odd units.

2.3 Titration of XULTOPHY 100/3.6

- After starting the recommended starting dosage of XULTOPHY 100/3.6 [see Dosage and Administration (2.2)], titrate the dosage upwards or downwards by two units (see Table 2) once weekly or twice weekly (every three to four days), based on the patient’s metabolic needs, blood glucose monitoring results, and glycemic control goal until the desired fasting plasma glucose is achieved.
- To minimize the risk of hypoglycemia or hyperglycemia, additional titration may be needed with changes in physical activity, meal patterns (i.e., macronutrient content or timing of food intake), or renal or hepatic function; during acute illness; or when used with other medications [see Warnings and Precautions (5.4), Drug Interactions (7)].

Table 2. Recommended Titration of XULTOPHY 100/3.6 (Once or Twice Weekly)

Self-Monitored Fasting Plasma Glucose | XULTOPHY 100/3.6 Dosage Adjustment
Above target range | + 2 units (2 units of insulin degludec and 0.072 mg of liraglutide)
Within target range | 0 units
Below target range | - 2 units (2 units of insulin degludec and 0.072 mg of liraglutide)

2.4 Recommendations Regarding Missed Doses

- Instruct patients who miss a dose of XULTOPHY 100/3.6 to resume the once-daily dosage regimen as prescribed with the next scheduled dose. Do not administer an extra dose or increase the dose to make up for the missed dose.
- If more than three days have elapsed since the last XULTOPHY 100/3.6 dose, reinitiate XULTOPHY 100/3.6 at the recommended starting dose to mitigate the risk of gastrointestinal adverse reactions associated with reinitiation of treatment [see Dosage and Administration (2.1, 2.2, 2.3)].

2.5 Important Administration Instructions

- The XULTOPHY 100/3.6 pen is for single-patient-use only [see Warnings and Precautions (5.3)].
- Train patients on proper use and injection technique before initiating XULTOPHY 100/3.6.
- Always check the label on the XULTOPHY 100/3.6 pen before administration [see Warnings and Precautions (5.5)].
- Inspect visually for particulate matter and discoloration prior to administration. Only use XULTOPHY 100/3.6 if the solution appears clear and colorless.
- Inject XULTOPHY 100/3.6 subcutaneously into the thigh, upper arm, or abdomen.
- Rotate injection sites within the same region from one injection to the next to reduce the risk of lipodystrophy and localized cutaneous amyloidosis. Do not inject into areas of lipodystrophy or localized cutaneous amyloidosis [see Warnings and Precautions (5.4), Adverse Reactions (6.1, 6.3)].
- During changes to a patient’s insulin regimen, increase the frequency of blood glucose monitoring [see Warnings and Precautions (5.4)].
- Use XULTOPHY 100/3.6 with caution in patients with visual impairment who may rely on audible clicks to dial their dose.
- The XULTOPHY 100/3.6 pen dials in one-unit increments.
- Do not administer XULTOPHY 100/3.6 intravenously or in an insulin infusion pump.
- Do not dilute or mix XULTOPHY 100/3.6 with any other insulin or solutions.
- Do not split the dose of XULTOPHY 100/3.6.

3 DOSAGE FORMS AND STRENGTHS

Injection: 100 units/mL insulin degludec and 3.6 mg/mL liraglutide available as a clear, colorless solution in a 3 mL prefilled, disposable, single-patient-use pen injector.

4 CONTRAINDICATIONS

XULTOPHY 100/3.6 is contraindicated:

- In patients with a personal or family history of medullary thyroid carcinoma (MTC) or in patients with Multiple Endocrine Neoplasia syndrome type 2 (MEN 2) [see Warnings and Precautions (5.1)].
- During episodes of hypoglycemia [see Warnings and Precautions (5.6)].
- In patients with hypersensitivity to insulin degludec, liraglutide, or any of the excipients in XULTOPHY 100/3.6. Serious hypersensitivity reactions including anaphylactic reactions and angioedema have been reported with liraglutide, one of the components of XULTOPHY 100/3.6 [see Warnings and Precautions (5.9)].

5 WARNINGS AND PRECAUTIONS

5.1 Risk of Thyroid C-cell Tumors

Liraglutide, one of the components of XULTOPHY 100/3.6, causes dose-dependent and treatment-duration-dependent thyroid C-cell tumors (adenomas and/or carcinomas) at clinically relevant exposures in both genders of rats and mice [see Nonclinical Toxicology (13.1)]. Malignant thyroid C-cell carcinomas were detected in rats and mice. It is unknown whether XULTOPHY 100/3.6 will cause thyroid C-cell tumors, including medullary thyroid carcinoma (MTC), in humans, as the human relevance of liraglutide-induced rodent thyroid C-cell tumors has not been determined.

Cases of MTC in patients treated with liraglutide have been reported in the postmarketing period; the data in these reports are insufficient to establish or exclude a causal relationship between MTC and liraglutide use in humans.

XULTOPHY 100/3.6 is contraindicated in patients with a personal or family history of MTC or in patients with MEN 2. Counsel patients regarding the potential risk for MTC with the use of XULTOPHY 100/3.6 and inform them of symptoms of thyroid tumors (e.g., a mass in the neck, dysphagia, dyspnea, persistent hoarseness).

Routine monitoring of serum calcitonin or using thyroid ultrasound is of uncertain value for early detection of MTC in patients treated with XULTOPHY 100/3.6. Such monitoring may increase the risk of unnecessary procedures, due to low test specificity for serum calcitonin and a high background incidence of thyroid disease. Significantly elevated serum calcitonin may indicate MTC and patients with MTC usually have calcitonin values >50 ng/L. If serum calcitonin is measured and found to be elevated, the patient should be further evaluated. Patients with thyroid nodules noted on physical examination or neck imaging should also be further evaluated.

5.2 Acute Pancreatitis

Acute pancreatitis, including fatal and non-fatal hemorrhagic or necrotizing pancreatitis, has been observed in patients treated with GLP-1 receptor agonists, including liraglutide, one of the components of XULTOPHY 100/3.6 [see Adverse Reactions (6)].

After initiation of XULTOPHY 100/3.6, observe patients carefully for signs and symptoms of acute pancreatitis, which may include persistent or severe abdominal pain (sometimes radiating to the back) and which may or may not be accompanied by nausea or vomiting. If pancreatitis is suspected, discontinue XULTOPHY 100/3.6 and initiate appropriate management.

5.3 Never Share a XULTOPHY 100/3.6 Pen Between Patients

XULTOPHY 100/3.6 pen must never be shared between patients, even if the needle is changed. Sharing of the pen poses a risk for transmission of blood-borne pathogens.

5.4 Hyperglycemia or Hypoglycemia with Changes in Insulin Regimen

Changes in an insulin regimen (e.g., insulin strength, manufacturer, type, injection site or method of administration) may affect glycemic control and predispose to hypoglycemia [see Warnings and Precautions (5.6)] or hyperglycemia. Repeated insulin injections into areas of lipodystrophy or localized cutaneous amyloidosis have been reported to result in hyperglycemia; and a sudden change in the injection site (to an unaffected area) has been reported to result in hypoglycemia [see Adverse Reactions (6.1, 6.3)]. Make any changes to a patient’s insulin regimen under close medical supervision with increased frequency of blood glucose monitoring. Advise patients who have repeatedly injected into areas of lipodystrophy or localized cutaneous amyloidosis to change the injection site to unaffected areas and closely monitor for hypoglycemia. Adjustments in concomitant oral anti-diabetic treatment may be needed. When initiating XULTOPHY 100/3.6, follow dosing recommendations [see Dosage and Administration (2.1, 2.2, 2.3)].

5.5 Overdose due to Medication Errors

XULTOPHY 100/3.6 contains two drugs: insulin degludec and liraglutide. Administration of more than 50 units of XULTOPHY 100/3.6 daily can result in overdose of the liraglutide component. Do not exceed the 1.8 mg maximum recommended dose of liraglutide or use with other GLP-1 receptor agonists.

Accidental mix-ups between insulin products have been reported. To avoid medication errors between XULTOPHY 100/3.6 (an insulin containing product) and other insulin products, instruct patients to always check the label before each injection.

5.6 Hypoglycemia

Hypoglycemia is the most common adverse reaction of insulin containing products, including XULTOPHY 100/3.6 [see Adverse Reactions (6.1)]. Severe hypoglycemia can cause seizures, may be life-threatening or cause death. Hypoglycemia can impair concentration ability and reaction time; this may place the patient and others at risk in situations where these abilities are important (e.g., driving or operating other machinery). XULTOPHY 100/3.6 (an insulin-containing product) or any insulin, should not be used during episodes of hypoglycemia [see Contraindications (4)].

Hypoglycemia can happen suddenly and symptoms may differ in each patient and change over time in the same patient. Symptomatic awareness of hypoglycemia may be less pronounced in patients with longstanding diabetes, in patients with diabetic neuropathy, in patients using drugs that block the sympathetic nervous system (e.g., beta-blockers) [see Drug Interactions (7.1)], or who experience recurrent hypoglycemia.

The long-acting effect of insulin degludec may delay recovery from hypoglycemia compared to shorter acting insulins.

Risk Factors for Hypoglycemia

The risk of hypoglycemia generally increases with intensity of glycemic control. The risk of hypoglycemia after an injection is related to the duration of action of the insulin [see Clinical Pharmacology (12.2)] and, in general, is highest when the glucose lowering effect of the insulin is maximal. As with all insulin containing products, the glucose lowering effect time course of XULTOPHY 100/3.6 may vary among different patients or at different times in the same patients and depends on many conditions, including the area of injection as well as the injection site blood supply and temperature.

Other factors which may increase the risk of hypoglycemia include changes in meal pattern (e.g., macronutrient content or timing of meals), changes in level of physical activity, or changes to concomitant drugs [see Drug Interactions (7.1)]. Patients with renal or hepatic impairment may be at higher risk of hypoglycemia [see Use in Specific Populations (8.6, 8.7)].

Risk Mitigation Strategies for Hypoglycemia

Patients and caregivers must be educated to recognize and manage hypoglycemia. Self-monitoring of blood glucose plays an essential role in the prevention and management of hypoglycemia. In patients at higher risk for hypoglycemia and patients who have reduced symptomatic awareness of hypoglycemia, increased frequency of blood glucose monitoring is recommended.

5.7 Acute Kidney Injury Due to Volume Depletion

There have been postmarketing reports of acute kidney injury, in some cases requiring hemodialysis, in patients treated with liraglutide, one of the components of XULTOPHY 100/3.6 [see Adverse Reactions (6.2)]. The majority of the reported events occurred in patients who experienced gastrointestinal reactions leading to dehydration such as nausea, vomiting, or diarrhea [see Adverse Reactions (6.1)]. Monitor renal function in patients reporting adverse reactions to XULTOPHY 100/3.6 that could lead to volume depletion, especially during dosage initiation and escalation of XULTOPHY 100/3.6.

5.8 Severe Gastrointestinal Adverse Reactions

Use of GLP-1 receptor agonists, including liraglutide, one of the components of XULTOPHY 100/3.6, has been associated with gastrointestinal adverse reactions, sometimes severe [see Adverse Reactions (6)]. In a XULTOPHY 100/3.6 clinical trial severe gastrointestinal adverse reactions were reported among patients receiving XULTOPHY 100/3.6 (0.8 %) and patients receiving the active comparators liraglutide (2.9%) and insulin degludec (0.2%) [see Clinical Studies (14.2)].Severe gastrointestinal adverse reactions have also been reported postmarketing with GLP-1 receptor agonists.XULTOPHY 100/3.6 is not recommended in patients with severe gastroparesis.

5.9 Hypersensitivity Reactions

Severe, life-threatening, generalized allergy, including anaphylaxis, angioedema, bronchospasm, hypotension, and shock can occur with insulins, including XULTOPHY 100/3.6. Allergic reactions (manifested with signs and symptoms such as urticaria, rash, pruritus) have been reported with XULTOPHY 100/3.6. There have been postmarketing reports of serious hypersensitivity reactions (e.g., anaphylactic reactions and angioedema) in patients treated with liraglutide, one of the components of XULTOPHY 100/3.6 [see Adverse Reactions (6.2)]. If a hypersensitivity reaction occurs, discontinue XULTOPHY 100/3.6; treat promptly per standard of care, and monitor until signs and symptoms resolve.

Anaphylaxis and angioedema have been reported with other GLP-1 receptor agonists. Use caution in a patient with a history of anaphylaxis or angioedema with another GLP-1 receptor agonist because it is unknown whether such patients will be predisposed to these reactions with XULTOPHY 100/3.6. XULTOPHY 100/3.6 is contraindicated in patients who have had hypersensitivity reactions to insulin degludec, liraglutide or one of the excipients of these products [see Contraindications (4)].

5.10 Acute Gallbladder Disease

Acute events of gallbladder disease such as cholelithiasis or cholecystitis have been reported in GLP-1 receptor agonist trials and postmarketing. In a cardiovascular outcomes trial (LEADER trial) [see Clinical Studies (14.4)], 3.1% of patients treated with liraglutide, one of the components of XULTOPHY 100/3.6, versus 1.9% of placebo treated patients reported an acute event of gallbladder disease, such as cholelithiasis or cholecystitis [see Adverse Reactions (6.1)]. If cholelithiasis is suspected, gallbladder studies and appropriate clinical follow-up are indicated.

5.11 Hypokalemia

All insulin-containing products, including XULTOPHY 100/3.6, cause a shift in potassium from the extracellular to intracellular space, possibly leading to hypokalemia. Untreated hypokalemia may cause respiratory paralysis, ventricular arrhythmia, and death. Monitor potassium levels in patients at risk for hypokalemia if indicated (e.g., patients using potassium-lowering medications, patients taking medications sensitive to serum potassium concentrations).

5.12 Fluid Retention and Congestive Heart Failure with Concomitant Use of a PPAR Gamma Agonist

Thiazolidinediones (TZDs), which are peroxisome proliferator-activated receptor (PPAR)-gamma agonists can cause dose related fluid retention, when used in combination with insulin containing products, including XULTOPHY 100/3.6. Fluid retention may lead to or exacerbate congestive heart failure. Patients treated with insulin containing products, including XULTOPHY 100/3.6 and a PPAR-gamma agonist should be observed for signs and symptoms of congestive heart failure. If congestive heart failure develops, it should be managed according to current standards of care and discontinuation or dose reduction of the PPAR-gamma agonist must be considered.

5.13 Pulmonary Aspiration During General Anesthesia or Deep Sedation

XULTOPHY 100/3.6 delays gastric emptying [see Clinical Pharmacology (12.1)]. There have been rare postmarketing reports of pulmonary aspiration in patients receiving GLP-1 receptor agonists undergoing elective surgeries or procedures requiring general anesthesia or deep sedation who had residual gastric contents despite reported adherence to preoperative fasting recommendations.

Available data are insufficient to inform recommendations to mitigate the risk of pulmonary aspiration during general anesthesia or deep sedation in patients taking XULTOPHY 100/3.6, including whether modifying preoperative fasting recommendations or temporarily discontinuing XULTOPHY 100/3.6 could reduce the incidence of retained gastric contents. Instruct patients to inform healthcare providers prior to any planned surgeries or procedures if they are taking XULTOPHY 100/3.6.

6 ADVERSE REACTIONS

The following serious adverse reactions are described below or elsewhere in the prescribing information:

- Risk of Thyroid C-cell Tumors [see Warnings and Precautions (5.1)]
- Acute Pancreatitis [see Warnings and Precautions (5.2)]
- Hypoglycemia [see Warnings and Precautions (5.6)]
- Acute Kidney Injury Due to Volume Depletion [see Warnings and Precautions (5.7)]
- Severe Gastrointestinal Adverse Reactions [see Warnings and Precautions (5.8)]
- Hypersensitivity Reactions [see Warnings and Precautions (5.9)]
- Acute Gallbladder Disease [see Warnings and Precautions (5.10)]
- Hypokalemia [see Warnings and Precautions (5.11)]
- Pulmonary Aspiration During General Anesthesia or Deep Sedation [see Warnings and Precautions (5.13)]

6.1 Clinical Trial Experience

Because clinical trials are conducted under widely varying conditions, adverse reaction rates observed in the clinical trials of a drug cannot be directly compared to rates in the clinical trials of another drug and may not reflect the rates observed in practice.

XULTOPHY 100/3.6

The data in Table 3 reflect the exposure of 1881 patients to XULTOPHY 100/3.6 and a mean duration of exposure of 33 weeks in trials NCT01336023, NCT01618162, NCT02773368, NCT01676116, NCT01392573, NCT01952145 [see Clinical Studies (14.2 and 14.3)]. The mean age was 57 years and 3% were older than 75 years; 53% were male, 75% were White, 6% were Black or African American and 16% were Hispanic or Latino. The mean body mass index (BMI) was 31.8 kg/m^2. The mean duration of diabetes was 9 years and the mean HbA1c at baseline was 8.2%. A history of neuropathy, ophthalmopathy, nephropathy and cardiovascular disease at baseline was reported in 25%, 12%, 7% and 6% respectively. The mean estimated glomerular filtration rate (eGFR) at baseline was 88.3 mL/min/1.73 m^2 and 6% of the patients had an eGFR less than 60 mL/min/1.73 m^2.

Table 3: Adverse Reactions Occurring in ≥5% of XULTOPHY 100/3.6-Treated Patients with Type 2 Diabetes Mellitus
 | XULTOPHY 100/3.6; N = 1881; %
Nasopharyngitis | 10
Headache | 9
Nausea | 8
Diarrhea | 8
Increased Lipase | 7
Upper respiratory tract infection | 6

Hypoglycemia

Hypoglycemia was the most commonly observed adverse reaction in patients treated with insulin and insulin containing products, including XULTOPHY 100/3.6 [see Warnings and Precautions (5.6)]. The number of reported hypoglycemia episodes depended on the definition of hypoglycemia used, insulin dose, intensity of glucose control, background therapies, and other intrinsic and extrinsic patient factors. For these reasons, comparing rates of hypoglycemia in clinical trials for XULTOPHY 100/3.6 with the incidence of hypoglycemia for other products may be misleading and also, may not be representative of hypoglycemia rates that will occur in clinical practice.

In the phase 3 clinical program [see Clinical Studies (14)], events of severe hypoglycemia were defined as an episode requiring assistance of another person to actively administer carbohydrate, glucagon, or other resuscitative actions (Table 4). Hypoglycemia episodes with a glucose level below 54 mg/dL associated with or without symptoms is shown in Table 4. No clinically important differences in risk of severe hypoglycemia between XULTOPHY 100/3.6 and comparators were observed in clinical trials.

Table 4. Hypoglycemia Episodes Reported in XULTOPHY 100/3.6-Treated Patients with T2DM

 | Patients naïve to basal insulin or GLP-1 receptor agonist |  |  | Patients currently on GLP-1 receptor agonist | Patients currently on basal insulin
 | XULTOPHY 100/3.6 NCT01336023 | XULTOPHY 100/3.6 NCT01618162 | XULTOPHY 100/3.6; NCT02773368 | XULTOPHY 100/3.6; NCT01676116 | XULTOPHY 100/3.6; NCT01392573 | XULTOPHY 100/3.6; NCT01952145
Total Subjects (N) | 825 | 288 | 209 | 291 | 199 | 278
Severe Hypoglycemia (%)† | 0.2 | 0.7 | 0.5 | 0.3 | 0.5 | 0
Hypoglycemia with a glucose level <54 mg/dL (%)* | 27.6 | 37.2 | 14.4 | 27.1 | 22.1 | 24.8
† Episode requiring assistance of another person to actively administer carbohydrate, glucagon, or other resuscitative actions.

* Episodes of hypoglycemia with a glucose level below 54 mg/dL that are associated with or without symptoms of hypoglycemia.

Gastrointestinal Adverse Reactions

Gastrointestinal adverse reactions including nausea, diarrhea, vomiting, constipation, dyspepsia, gastritis, abdominal pain, flatulence, eructation, gastroesophageal reflux disease, abdominal distension and decreased appetite have been reported in patients treated with XULTOPHY 100/3.6. In a XULTOPHY 100/3.6 clinical trial severe gastrointestinal adverse reactions were reported among patients receiving XULTOPHY 100/3.6 (0.8%) and patients receiving the active comparators liraglutide (2.9%) and insulin degludec (0.2%) [see Clinical Studies (14.2)].Gastrointestinal adverse reactions may occur more frequently at the beginning of XULTOPHY 100/3.6 therapy and diminish within a few days or weeks on continued treatment.

Papillary thyroid carcinoma

Liraglutide

In glycemic control trials of liraglutide, there were 7 reported cases of papillary thyroid carcinoma in patients treated with liraglutide and 1 case in a comparator-treated patient (1.5 vs. 0.5 cases per 1,000 patient years). Most of these papillary thyroid carcinomas were <1 cm in greatest diameter and were diagnosed in surgical pathology specimens after thyroidectomy prompted by findings on protocol-specified screening with serum calcitonin or thyroid ultrasound.

Pancreatitis

Liraglutide

In glycemic control trials of liraglutide, there have been 13 cases of pancreatitis among liraglutide-treated patients and 1 case in a comparator (glimepiride) treated patient (2.7 vs. 0.5 cases per 1,000 patient-years). Nine of the 13 cases with liraglutide were reported as acute pancreatitis and four were reported as chronic pancreatitis. In one case in a liraglutide-treated patient, pancreatitis, with necrosis, was observed and led to death; however clinical causality could not be established. Some patients had other risk factors for pancreatitis, such as a history of cholelithiasis or alcohol abuse.

Cholelithiasis and cholecystitis

Liraglutide

In glycemic control trials of liraglutide, the incidence of cholelithiasis was 0.3% in both liraglutide-treated and placebo-treated patients. The incidence of cholecystitis was 0.2% in both liraglutide treated and placebo-treated patients.

In a cardiovascular outcomes trial (LEADER trial) [see Clinical Studies (14.4)], the incidence of cholelithiasis was 1.5% (3.9 cases per 1,000 patient years of observation) in liraglutide-treated and 1.1% (2.8 cases per 1,000 patient years of observation) in placebo-treated patients, both on a background of standard of care. The incidence of acute cholecystitis was 1.1% (2.9 cases per 1,000 patient years of observation) in liraglutide-treated and 0.7% (1.9 cases per 1,000 patient years of observation) in placebo-treated patients. The majority of events required hospitalization or cholecystectomy.

Initiation of insulin containing products and intensification of glucose control

Intensification or rapid improvement in glucose control has been associated with a transitory, reversible ophthalmologic refraction disorder, worsening of diabetic retinopathy, and acute painful peripheral neuropathy. However, long-term glycemic control decreases the risk of diabetic retinopathy and neuropathy.

Lipodystrophy

Long-term use of insulin containing products, including XULTOPHY 100/3.6, can cause lipodystrophy at the site of repeated injections. Lipodystrophy includes lipohypertrophy (thickening of adipose tissue) and lipoatrophy (thinning of adipose tissue), and may affect absorption [see Dosage and Administration (2.5)].

Peripheral Edema

XULTOPHY 100/3.6 may cause sodium retention and edema, particularly if previously poor metabolic control is improved rapidly by intensified therapy.

Weight Gain

Weight gain can occur with insulin containing products, including XULTOPHY 100/3.6, and has been attributed to the anabolic effects of insulin. In study A, after 26 weeks of treatment, patients converting to XULTOPHY 100/3.6 from liraglutide had a mean increase in body weight of 2 kg.

Injection Site reactions

As with any insulin and GLP-1 receptor agonist-containing products, patients taking XULTOPHY 100/3.6 may experience injection site reactions, including injection site hematoma, pain, hemorrhage, erythema, nodules, swelling, discoloration, pruritus, warmth, and injection site mass. In the clinical program, the proportion of injection site reactions occurring in patients treated with XULTOPHY 100/3.6 was 2.6%. These reactions were usually mild and transitory and they normally disappear during continued treatment.

Hypersensitivity Reactions

Severe, life-threatening, generalized allergy, including anaphylaxis, generalized skin reactions, angioedema, bronchospasm, hypotension, and shock have occurred with insulin, including XULTOPHY 100/3.6 and may be life threatening [see Warnings and Precautions (5.8)]. Hypersensitivity (manifested with swelling of tongue and lips, diarrhea, nausea, tiredness, and itching) and urticaria were reported.

Laboratory tests

Bilirubin

Liraglutide

In the five glycemic control trials of at least 26 weeks duration, mildly elevated serum bilirubin concentrations (elevations to no more than twice the upper limit of the reference range) occurred in 4.0% of liraglutide-treated patients, 2.1% of placebo-treated patients and 3.5% of active-comparator-treated patients. This finding was not accompanied by abnormalities in other liver tests. The significance of this isolated finding is unknown.

Calcitonin

XULTOPHY 100/3.6

Calcitonin, a biological marker of MTC, was measured throughout the XULTOPHY 100/3.6 clinical development program. Among patients with pretreatment calcitonin <20 ng/L, calcitonin elevations to >20 ng/L occurred in 0.7% of XULTOPHY 100/3.6-treated patients, 0.7% of placebo-treated patients, and 1.1% and 0.7% of active-comparator-treated patients (basal insulins and GLP-1s respectively). The clinical significance of these findings is unknown.

Liraglutide

Calcitonin, a biological marker of MTC, was measured throughout the liraglutide clinical development program. At the end of the glycemic control trials, adjusted mean serum calcitonin concentrations were higher in liraglutide-treated patients compared to placebo-treated patients but not compared to patients receiving active comparator. Between group differences in adjusted mean serum calcitonin values were approximately 0.1 ng/L or less. Among patients with pretreatment calcitonin <20 ng/L, calcitonin elevations to >20 ng/L occurred in 0.7% of liraglutide-treated patients, 0.3% of placebo-treated patients, and 0.5% of active-comparator-treated patients. The clinical significance of these findings is unknown.

Lipase and Amylase

Liraglutide

In one glycemic control trial in renal impairment patients, a mean increase of 33% for lipase and 15% for amylase from baseline was observed for liraglutide-treated patients while placebo-treated patients had a mean decrease in lipase of 3% and a mean increase in amylase of 1%.

In a cardiovascular outcomes trial (LEADER trial) [see Clinical Studies (14.4)], serum lipase and amylase were routinely measured. Among liraglutide-treated patients, 7.9% had a lipase value at any time during treatment of greater than or equal to 3 times the upper limit of normal compared with 4.5% of placebo-treated patients, and 1% of liraglutide-treated patients had an amylase value at any time during treatment of greater than or equal to 3 times the upper limit of normal versus 0.7% of placebo-treated patients.

The clinical significance of elevations in lipase or amylase with liraglutide is unknown in the absence of other signs and symptoms of pancreatitis [see Warnings and Precautions (5.2)].

Vital signs

Mean increases from baseline in heart rate of 2 to 3 beats per minute have been observed with XULTOPHY 100/3.6 which is attributable to the liraglutide component.

6.2 Postmarketing Experience

The following additional adverse reactions have been reported during post-approval use. Because these events are reported voluntarily from a population of uncertain size, it is generally not possible to reliably estimate their frequency or establish a causal relationship to drug exposure.

Insulin degludec

Localized cutaneous amyloidosis at the injection site has occurred. Hyperglycemia has been reported with repeated insulin injections into areas of localized cutaneous amyloidosis; hypoglycemia has been reported with a sudden change to an unaffected injection site.

Liraglutide

- Gastrointestinal: Acute pancreatitis; hemorrhagic and necrotizing pancreatitis sometimes resulting in death; ileus, and nausea, vomiting and diarrhea leading to dehydration, intestinal obstruction, severe constipation including fecal impaction
- Hepatobiliary: Elevations of liver enzymes, hyperbilirubinemia, cholestasis, cholecystitis, cholelithiasis requiring cholecystectomy, hepatitis
- Hypersensitivity: Angioedema, anaphylactic reactions, rash, pruritus
- Neoplasms: Medullary thyroid carcinoma
- Neurologic: Dysgeusia, dysesthesia, dizziness
- Pulmonary: Pulmonary aspiration has occurred in patients receiving GLP-1 receptor agonists undergoing elective surgeries or procedures requiring general anesthesia or deep sedation.
- Renal: Acute renal failure or worsening of chronic renal failure, sometimes requiring hemodialysis; and increased serum creatinine
- Skin and subcutaneous tissue: Cutaneous amyloidosis, alopecia

7 DRUG INTERACTIONS

7.1 Medications that Can Affect Glucose Metabolism

A number of medications affect glucose metabolism and may require dose adjustment of XULTOPHY 100/3.6 and particularly close monitoring [see Dosage and Administration (2.2), Warnings and Precautions (5.6)].

Drugs That May Increase the Risk of Hypoglycemia
Drugs: | Antidiabetic agents, ACE inhibitors, angiotensin II receptor blocking agents, disopyramide, fibrates, fluoxetine, monoamine oxidase inhibitors, pentoxifylline, pramlintide, salicylates, somatostatin analogs (e.g., octreotide), and sulfonamide antibiotics
Intervention: | Dosage reductions and increased frequency of glucose monitoring may be required when XULTOPHY 100/3.6 is coadministered with these drugs.
Drugs That May Decrease the Blood Glucose Lowering Effect of XULTOPHY 100/3.6
Drugs: | Atypical antipsychotics (e.g., olanzapine and clozapine), corticosteroids, danazol, diuretics, estrogens, glucagon, isoniazid, niacin, oral contraceptives, phenothiazines, progestogens (e.g., in oral contraceptives), protease inhibitors, somatropin, sympathomimetic agents (e.g., albuterol, epinephrine, terbutaline), and thyroid hormones.
Intervention: | Dosage increases and increased frequency of glucose monitoring may be required when XULTOPHY 100/3.6 is coadministered with these drugs.
Drugs That May Increase or Decrease the Blood Glucose Lowering Effect of XULTOPHY 100/3.6
Drugs: | Alcohol, beta-blockers, clonidine, and lithium salts. Pentamidine may cause hypoglycemia, which may sometimes be followed by hyperglycemia.
Intervention: | Dosage adjustment and increased frequency of glucose monitoring may be required when XULTOPHY 100/3.6 is coadministered with these drugs.
Drugs That May Blunt Signs and Symptoms of Hypoglycemia
Drugs: | Beta-blockers, clonidine, guanethidine, and reserpine
Intervention: | Increased frequency of glucose monitoring may be required when XULTOPHY 100/3.6 is coadministered with these drugs.

7.2 Effects of Delayed Gastric Emptying on Oral Medications

Liraglutide-containing products, including XULTOPHY 100/3.6, cause a delay of gastric emptying, and thereby have the potential to impact the absorption of concomitantly administered oral medications. In clinical pharmacology trials, liraglutide did not affect the absorption of the tested orally administered medications to any clinically relevant degree [see Clinical Pharmacology (12.3)]. Nonetheless, caution should be exercised when oral medications are concomitantly administered with liraglutide containing products.

8 USE IN SPECIFIC POPULATIONS

8.1 Pregnancy

Risk Summary

Based on animal reproduction studies, there may be risks to the fetus from exposure to liraglutide during pregnancy. XULTOPHY 100/3.6 should be used during pregnancy only if the potential benefit justifies the potential risk to the fetus.

There are no available data with XULTOPHY 100/3.6, insulin degludec or liraglutide in pregnant women to inform a drug associated risk for major birth defects and miscarriage. There are clinical considerations regarding the risks of poorly controlled diabetes in pregnancy (see Clinical Considerations).

For insulin degludec, rats and rabbits were exposed in animal reproduction studies at 5 times (rat) and 10 times (rabbit) the human exposure at a dose of 0.75 U/kg/day. No adverse outcomes were observed for pregnant animals and offspring (see Data).

For liraglutide, animal reproduction studies identified increased adverse developmental outcomes from exposure during pregnancy. Liraglutide exposure was associated with early embryonic deaths and an imbalance in some fetal abnormalities in pregnant rats administered liraglutide during organogenesis at doses that approximate clinical exposures at the maximum recommended human dose (MRHD) of 1.8 mg/day. In pregnant rabbits administered liraglutide during organogenesis, decreased fetal weight and an increased incidence of major fetal abnormalities were seen at exposures below the human exposures at the MRHD (see Data).

In the U.S. general population, the estimated background risk of major birth defects and miscarriage in clinically recognized pregnancies is 2 to 4% and 15 to 20%, respectively. The estimated background risk of major birth defects is 6 to 10% in women with pregestational diabetes with a peri-conceptional HbA1c >7 and has been reported to be as high as 20 to 25% in women with a peri-conceptional HbA1c >10. The estimated background risk of miscarriage for the indicated population is unknown.

Clinical Considerations

Disease-Associated Maternal and/or Embryo/fetal Risk

Hypoglycemia and hyperglycemia occur more frequently during pregnancy in patients with pre-gestational diabetes. Poorly controlled diabetes in pregnancy increases the maternal risk for diabetic ketoacidosis, preeclampsia, spontaneous abortions, preterm delivery, and delivery complications. Poorly controlled diabetes mellitus increases the fetal risk for major birth defects, stillbirth, macrosomia related morbidity.

Data

Animal Data

Insulin degludec

Insulin degludec was investigated in studies covering fertility, embryo-fetal development and pre- and post-natal development in rats and during the period of embryo-fetal development in rabbits. Human insulin (NPH insulin) was included as comparator. In these studies insulin degludec was given subcutaneously at up to 21 U/kg/day in rats and 3.3 U/kg/day in rabbits, resulting in 5 times (rat) and 10 times (rabbit) the human exposure (AUC) at a human subcutaneous dose of 0.75 U/kg/day. Overall the effects of insulin degludec were similar to those observed with human insulin.

Liraglutide

Female rats given subcutaneous doses of 0.1, 0.25 and 1.0 mg/kg/day liraglutide beginning 2 weeks before mating through gestation day 17 had estimated systemic exposures 0.8-, 3-, and 11-times the human exposure at the MRHD based on plasma AUC comparison. The number of early embryonic deaths in the 1 mg/kg/day group increased slightly. Fetal abnormalities and variations in kidneys and blood vessels, irregular ossification of the skull, and a more complete state of ossification occurred at all doses. Mottled liver and minimally kinked ribs occurred at the highest dose. The incidence of fetal malformations in liraglutide-treated groups exceeding concurrent and historical controls were misshapen oropharynx and/or narrowed opening into larynx at 0.1 mg/kg/day and umbilical hernia at 0.1 and 0.25 mg/kg/day.

Pregnant rabbits given subcutaneous doses of 0.01, 0.025 and 0.05 mg/kg/day liraglutide from gestation day 6 through day 18 inclusive, had estimated systemic exposures less than the human exposure at the MRHD of 1.8 mg/day at all doses, based on plasma AUC. Liraglutide decreased fetal weight and dose dependently increased the incidence of total major fetal abnormalities at all doses. The incidence of malformations exceeded concurrent and historical controls at 0.01 mg/kg/day (kidneys, scapula), ≥0.01 mg/kg/day (eyes, forelimb), 0.025 mg/kg/day (brain, tail and sacral vertebrae, major blood vessels and heart, umbilicus), ≥0.025 mg/kg/day (sternum) and at 0.05 mg/kg/day (parietal bones, major blood vessels). Irregular ossification and/or skeletal abnormalities occurred in the skull and jaw, vertebrae and ribs, sternum, pelvis, tail, and scapula; and dose-dependent minor skeletal variations were observed. Visceral abnormalities occurred in blood vessels, lung, liver, and esophagus. Bilobed or bifurcated gallbladder was seen in all treatment groups, but not in the control group.

In pregnant female rats given subcutaneous doses of 0.1, 0.25 and 1.0 mg/kg/day liraglutide from gestation day 6 through weaning or termination of nursing on lactation day 24, estimated systemic exposures were 0.8-, 3-, and 11-times human exposure at the MRHD of 1.8 mg/day, based on plasma AUC. A slight delay in parturition was observed in the majority of treated rats. Group mean body weight of neonatal rats from liraglutide-treated dams was lower than neonatal rats from control group dams. Bloody scabs and agitated behavior occurred in male rats descended from dams treated with 1 mg/kg/day liraglutide. Group mean body weight from birth to postpartum day 14 trended lower in F2 generation rats descended from liraglutide-treated rats compared to F2 generation rats descended from controls, but differences did not reach statistical significance for any group.

8.2 Lactation

Risk Summary

There are no data on the presence of liraglutide or insulin degludec in human milk, the effects on the breastfed infant, or the effects on milk production. In lactating rats, insulin degludec and liraglutide, the two components of XULTOPHY 100/3.6, were present in milk.

The developmental and health benefits of breastfeeding should be considered along with the mother’s clinical need for XULTOPHY 100/3.6 and any potential adverse effects on the breastfed infant from XULTOPHY 100/3.6 or from the underlying maternal condition.

Data

Insulin degludec

In lactating rats, insulin degludec was present in milk at a concentration lower than that in plasma.

Liraglutide

In lactating rats, liraglutide was present unchanged in milk at concentrations approximately 50% of maternal plasma concentrations.

8.4 Pediatric Use

Safety and effectiveness of XULTOPHY 100/3.6 have not been established in pediatric patients.

8.5 Geriatric Use

Of the total number of 1,881 subjects in clinical studies of XULTOPHY 100/3.6, 375 (19.9%) were 65 years and over, while 52 (2.8%) were 75 years and over [see Clinical Studies (14)]. No overall differences in safety or effectiveness of XULTOPHY 100/3.6 were observed between patients 65 years of age and older and younger patients.

Age had no clinically relevant effect on the pharmacokinetics of XULTOPHY 100/3.6 [see Clinical Pharmacology (12.3)].

In geriatric patients with diabetes, the initial dosing, dose increments, and maintenance dosage should be conservative to avoid hypoglycemic reactions. Hypoglycemia may be more difficult to recognize in geriatric patients.

8.6 Renal Impairment

XULTOPHY 100/3.6

There is limited experience with XULTOPHY 100/3.6 in patients with mild and moderate kidney impairment and when used in these patients, additional glucose monitoring and XULTOPHY 100/3.6 dose adjustments may be required on an individual basis. XULTOPHY 100/3.6 has not been studied in patients with severe kidney impairment [see Warnings and Precautions (5.7), Clinical Pharmacology (12.3)].

Insulin degludec

No clinically relevant difference in the pharmacokinetics of insulin degludec was identified in a study comparing healthy subjects and subjects with kidney impairment including subjects with end stage kidney disease.

Liraglutide

The safety and efficacy of liraglutide was evaluated in a 26-week clinical study that included patients with moderate kidney impairment (eGFR 30 to 60 mL/min/1.73 m^2). In the liraglutide treatment arm of a cardiovascular outcomes trial (LEADER trial) [see Clinical Studies (14.4)], 1932 (41.4%) patients had mild kidney impairment, 999 (21.4%) patients had moderate renal impairment and 117 (2.5%) patients had severe kidney impairment at baseline. No overall differences in safety or efficacy were seen in these patients compared to patients with normal kidney function.

There is limited experience with liraglutide in patients with end stage kidney disease.

8.7 Hepatic Impairment

XULTOPHY 100/3.6

XULTOPHY 100/3.6 has not been studied in patients with hepatic impairment.

Insulin degludec

No clinically relevant difference in the pharmacokinetics of insulin degludec, one of the components of XULTOPHY 100/3.6, was identified in a study comparing healthy subjects and subjects with hepatic impairment (mild, moderate, and severe hepatic impairment) [see Clinical Pharmacology (12.3)].

Liraglutide

There is limited experience in patients with mild, moderate or severe hepatic impairment with liraglutide, one of the components of XULTOPHY 100/3.6 [see Clinical Pharmacology (12.3)].

10 OVERDOSAGE

Hypoglycemia (from insulin and liraglutide) and gastrointestinal adverse reactions (from liraglutide) may develop if a patient is dosed with more XULTOPHY 100/3.6 than required.

An excess of insulin-containing products like XULTOPHY 100/3.6 relative to food intake, energy expenditure, or both may lead to severe and sometimes prolonged and life-threatening hypoglycemia and hypokalemia [see Warnings and Precautions (5.6, 5.10)]. Mild episodes of hypoglycemia usually can be treated with oral glucose. Lowering the drug dosage, and adjustments in meal patterns, or exercise may be needed. More severe episodes of hypoglycemia with coma, seizure, or neurologic impairment may be treated with intramuscular/subcutaneous glucagon for emergency use or concentrated intravenous glucose. After apparent clinical recovery from hypoglycemia, continued observation and additional carbohydrate intake may be necessary to avoid reoccurrence of hypoglycemia. Hypokalemia must be corrected appropriately.

Overdoses have been reported in clinical trials and postmarketing use of liraglutide, one of the components of XULTOPHY 100/3.6. Effects have included severe nausea and severe vomiting. In the event of overdosage, consider contacting the Poison Help line (1-800-222-1222) or a medical toxicologist for additional overdosage management recommendations. Initiate appropriate supportive treatment according to the patient’s clinical signs and symptoms.

11 DESCRIPTION

Insulin degludec

Insulin degludec is a long-acting basal human insulin analog. Insulin degludec is produced by a process that includes expression of recombinant DNA in Saccharomyces cerevisiae followed by chemical modification.

Insulin degludec differs from human insulin in that the amino acid threonine in position B30 has been omitted and a side-chain consisting of glutamic acid and a C16 fatty acid has been attached (chemical name: LysB29(Nε-hexadecandioyl-γ-Glu) des(B30) human insulin). Insulin degludec has a molecular formula of C274H411N65O81S6 and a molecular weight of 6.104 kDa. It has the following structure:

Figure 1. Structural Formula of Insulin degludec

Liraglutide

Liraglutide is an analog of human GLP-1 and acts as a GLP-1 receptor agonist. The peptide precursor of liraglutide, produced by a process that includes expression of recombinant DNA in Saccharomyces cerevisiae, has been engineered to be 97% homologous to native human GLP-1 by substituting arginine for lysine at position 34. Liraglutide is made by attaching a C16 fatty acid (palmitic acid) with a glutamic acid spacer on the remaining lysine residue at position 26 of the peptide precursor. The molecular formula of liraglutide is C172H265N43O51 and the molecular weight is 3.751 kDa. It has the following structure:

Figure 2. Structural Formula of Liraglutide

XULTOPHY 100/3.6 (insulin degludec and liraglutide) injection, for subcutaneous use, is a combination of a long-acting basal human insulin analog, insulin degludec, and a GLP-1 receptor agonist, liraglutide.

XULTOPHY 100/3.6 is a sterile, aqueous, clear, and colorless solution. Each prefilled pen contains 3 mL equivalent to 300 units insulin degludec and 10.8 mg liraglutide. Each mL contains 100 units insulin degludec and 3.6 mg liraglutide.

XULTOPHY 100/3.6 contains the following inactive ingredients per mL: glycerol (19.7 mg), phenol (5.7 mg), zinc (55 mcg), and Water for Injection, USP. XULTOPHY 100/3.6 has a pH of approximately 8.15. Hydrochloric acid or sodium hydroxide may be added to adjust pH.

12 CLINICAL PHARMACOLOGY

12.1 Mechanism of Action

XULTOPHY 100/3.6

XULTOPHY 100/3.6 is a combination product consisting of insulin degludec and liraglutide.

Insulin degludec

The primary activity of insulin degludec is the regulation of glucose metabolism. Insulin and its analogs lower blood glucose by stimulating peripheral glucose uptake, especially by skeletal muscle and fat, and by inhibiting hepatic glucose production. Insulin also inhibits lipolysis and proteolysis, and enhances protein synthesis.

Liraglutide

Liraglutide is a GLP-1 receptor agonist that increases glucose-dependent insulin release, decreases glucagon secretion, and slows gastric emptying.

12.2 Pharmacodynamics

Following a single-dose administration, XULTOPHY 100/3.6 has a duration of action reflecting the combination of the individual glucodynamic action profiles of insulin degludec and liraglutide.

Following once-daily administration, XULTOPHY 100/3.6 lowers fasting plasma glucose levels and postprandial glucose levels.

Cardiac Electrophysiology (QTc):

XULTOPHY 100/3.6

The effect of XULTOPHY 100/3.6 on QTc has not been studied.

Liraglutide

The effect of liraglutide, one of the components of XULTOPHY 100/3.6, on cardiac repolarization was tested in a QTc study. Liraglutide, at steady state concentrations with daily doses up to 1.8 mg, did not produce QTc prolongation.

12.3 Pharmacokinetics

Overall, the pharmacokinetics of insulin degludec and liraglutide were not affected in a clinically relevant manner when administered as XULTOPHY 100/3.6.

Absorption

In patients with type 2 diabetes mellitus (mean body weight 87.5 kg) reaching the maximum daily dose (50 units/1.8 mg) of XULTOPHY 100/3.6, the estimated mean steady-state exposure (AUC 0-24 h) of insulin degludec was 113 h*nmol/L and of liraglutide 1227 h*ng/mL based on population pharmacokinetic analysis. The corresponding maximum concentrations were 5196 pmol/L for insulin degludec and 55 ng/mL for liraglutide. Steady state concentrations of insulin degludec and liraglutide are reached after 2-3 days of daily administration.

Distribution

Insulin degludec and liraglutide are extensively bound to plasma proteins >99% and >98%, respectively.

Elimination

The half-life of insulin degludec is approximately 25 hours and the half-life of liraglutide is approximately 13 hours.

Metabolism

Insulin degludec

Degradation of insulin degludec is similar to that of human insulin; all metabolites formed are inactive.

Liraglutide

During the initial 24 hours following administration of a single [^3H]-liraglutide dose to healthy subjects, the major component in plasma was intact liraglutide. Liraglutide is endogenously metabolized in a similar manner to large proteins without a specific organ as a major route of elimination.

Specific Populations

Geriatric Patients

Age had no clinically relevant effect on the pharmacokinetics of XULTOPHY 100/3.6 based on results from a population pharmacokinetic analysis including adult patients up to 83 years treated with XULTOPHY 100/3.6 [see Use in Specific Populations (8.5)].

Male and Female Patients

There were no clinically relevant differences in the pharmacokinetics of XULTOPHY 100/3.6 in male and female patients, based on results from a population pharmacokinetic analysis.

Racial or Ethnic Groups

There were no clinically relevant differences in the pharmacokinetics of XULTOPHY 100/3.6 between the racial and ethnic groups investigated, based on results from a population pharmacokinetic analysis.

Body weight

The effect of body weight on the exposure level of the components of XULTOPHY 100/3.6 was investigated in the population pharmacokinetic analysis. Exposure levels decreased with increase in baseline body weight for both insulin degludec and liraglutide.

Patients with Renal Impairment

XULTOPHY 100/3.6

There is limited experience with XULTOPHY 100/3.6 in patients with mild and moderate renal impairment. XULTOPHY 100/3.6 has not been studied in patients with severe renal impairment [see Warnings and Precautions (5.7)].

Insulin degludec

Insulin degludec has been studied in a pharmacokinetic study in 32 subjects (n=6/group) with normal or impaired renal function/end-stage renal disease following administration of a single dose (0.4 U/kg) of insulin degludec. Renal function was defined using creatinine clearance (Clcr) as follows: >80 mL/min (normal), 50-80 mL/min (mild), 30-50 mL/min (moderate) and <30 mL/min (severe). Subjects requiring dialysis were classified as having end-stage renal disease (ESRD). Total exposure (AUCIDeg,0-120h,SD) of insulin degludec was similar in subjects with normal and impaired renal function. No clinically relevant difference in the pharmacokinetics of insulin degludec was identified between healthy subjects and subjects with renal impairment. Hemodialysis did not affect clearance of insulin degludec (CL/FIDeg,SD) in subjects with ESRD [see Warnings and Precautions (5.7)].

Liraglutide

The single-dose pharmacokinetics of liraglutide were evaluated in subjects with varying degrees of renal impairment. Subjects with mild (estimated creatinine clearance 50-80 mL/min) to severe (estimated creatinine clearance <30 mL/min) renal impairment and subjects with end-stage renal disease requiring dialysis were included in the trial. Compared to healthy subjects, liraglutide AUC in mild, moderate, and severe renal impairment and in end-stage renal disease was on average 35%, 19%, 29% and 30% lower, respectively [see Warnings and Precautions (5.7)].

Patients with Hepatic Impairment

XULTOPHY 100/3.6

XULTOPHY 100/3.6 has not been studied in patients with hepatic impairment.

Insulin degludec

Insulin degludec has been studied in a pharmacokinetic study in 24 subjects (n=6/group) with normal or impaired hepatic function (mild, moderate, and severe hepatic impairment) following administration of a single dose (0.4 U/kg) of insulin degludec. Hepatic function was defined using Child-Pugh Scores ranging from 5 (mild hepatic impairment) to 15 (severe hepatic impairment). No clinically relevant differences in the pharmacokinetics of insulin degludec were identified between healthy subjects and subjects with hepatic impairment [see Hepatic Impairment (8.7)].

Liraglutide

The single-dose pharmacokinetics of liraglutide were evaluated in subjects with varying degrees of hepatic impairment. Subjects with mild (Child Pugh score 5-6) to severe (Child Pugh score >9) hepatic impairment were included in the trial. Compared to healthy subjects, liraglutide AUC in subjects with mild, moderate and severe hepatic impairment was on average 11%, 14% and 42% lower, respectively.

Drug Interaction Studies

In vitro assessment of drug-drug interactions

In vitro data suggest that the potential for pharmacokinetic drug interactions related to CYP interaction and protein binding is low for both the liraglutide and insulin degludec components of XULTOPHY 100/3.6.

The delay of gastric emptying with liraglutide one of the components of XULTOPHY 100/3.6 may influence absorption of concomitantly administered oral medicinal products. Interaction studies did not show any clinically relevant delay of absorption.

In vivo assessment of drug-drug interactions

Liraglutide

The drug-drug interaction studies were performed at steady state with liraglutide 1.8 mg/day. Before administration of concomitant treatment, subjects underwent a 0.6 mg weekly dose increase to reach the maximum dose of 1.8 mg/day. Administration of the interacting drugs was timed so that Cmax of liraglutide (8-12 h) would coincide with the absorption peak of the coadministered drugs.

Digoxin

A single dose of digoxin 1 mg was administered 7 hours after the dose of liraglutide at steady state. The concomitant administration with liraglutide resulted in a reduction of digoxin AUC by 16%; Cmax decreased by 31%. Digoxin median time to maximal concentration (Tmax) was delayed from 1 h to 1.5 h.

Lisinopril

A single dose of lisinopril 20 mg was administered 5 minutes after the dose of liraglutide at steady state. The co-administration with liraglutide resulted in a reduction of lisinopril AUC by 15%; Cmax decreased by 27%. Lisinopril median Tmax was delayed from 6 h to 8 h with liraglutide.

Atorvastatin

Liraglutide did not change the overall exposure (AUC) of atorvastatin following a single dose of atorvastatin 40 mg, administered 5 hours after the dose of liraglutide at steady state. Atorvastatin Cmax was decreased by 38% and median Tmax was delayed from 1 to 3 hours with liraglutide.

Acetaminophen

Liraglutide did not change the overall exposure (AUC) of acetaminophen following a single dose of acetaminophen 1,000 mg, administered 8 hours after the dose of liraglutide at steady state. Acetaminophen Cmax was decreased by 31% and median Tmax was delayed up to 15 minutes.

Griseofulvin

Liraglutide did not change the overall exposure (AUC) of griseofulvin following co-administration of a single dose of griseofulvin 500 mg with liraglutide at steady state. Griseofulvin Cmax increased by 37% while median Tmax did not change.

Oral Contraceptives

A single dose of an oral contraceptive combination product containing 0.03 mg ethinylestradiol and 0.15 mg levonorgestrel was administered under fed conditions and 7 hours after the dose of liraglutide at steady state. Liraglutide lowered ethinylestradiol and levonorgestrel Cmax by 12% and 13%, respectively. There was no effect of liraglutide on the overall exposure (AUC) of ethinylestradiol. Liraglutide increased the levonorgestrel AUC0-∞ by 18%. Liraglutide delayed Tmax for both ethinylestradiol and levonorgestrel by 1.5 hours.

12.6 Immunogenicity

The observed incidence of anti-drug antibodies is highly dependent on the sensitivity and specificity of the assay. Differences in assay methods preclude meaningful comparisons of the incidence of anti-drug antibodies in the studies described below with the incidence of anti-drug antibodies in other studies, including those of XULTOPHY 100/3.6, insulin degludec, or liraglutide.

XULTOPHY 100/3.6

Administration of XULTOPHY 100/3.6 may cause formation of antibodies against insulin degludec and/or liraglutide. In rare cases, the presence of such antibodies may necessitate adjustment of the XULTOPHY 100/3.6 dose in order to correct a tendency to hyper- or hypoglycemia. During the 26-52-week clinical trials where antibodies were measured in patients receiving XULTOPHY 100/3.6, 90/812 (11%) patients were positive for insulin degludec specific antibodies at end of treatment vs. 22/936 (2%) at baseline, 250/811 (31%) patients were positive for antibodies cross-reacting with human insulin at end of treatment vs. 136/930 (15%) at baseline. 17/815 (2%) of patients developed treatment induced anti-liraglutide antibodies. No patients had preexisting anti-liraglutide antibodies. Antibody formation has not been associated with reduced efficacy of XULTOPHY 100/3.6.

Liraglutide

A subset of liraglutide-treated patients (1104 of 2501, 44%) in five adult double-blind clinical trials of 26-weeks duration or longer were tested for the presence of anti-liraglutide antibodies at the end of treatment [see Clinical Studies (14.1)] and 102/1104 (9%) of liraglutide-treated patients developed anti-liraglutide antibodies. Of these 102 liraglutide-treated patients, 56 (5%) patients developed antibodies that cross-reacted with native GLP-1. These cross-reacting antibodies were not tested for neutralizing effect against native GLP-1, and thus the potential for clinically significant neutralization of native GLP-1 was not assessed. Antibodies that had a neutralizing effect on liraglutide in an in vitro assay occurred in 12 (1%) of the liraglutide-treated patients. There was no identified clinically significant effect of anti-liraglutide antibodies on effectiveness of liraglutide.

In five double-blind glycemic control trials of liraglutide, events from a composite of adverse events potentially related to immunogenicity (e.g., urticaria, angioedema) occurred among 0.8% of liraglutide-treated patients and among 0.4% of comparator-treated patients. Urticaria accounted for approximately one-half of the events in this composite for liraglutide-treated patients. Patients who developed anti-liraglutide antibodies were not more likely to develop events from the immunogenicity events composite than were patients who did not develop anti-liraglutide antibodies.

In a cardiovascular outcomes trial (LEADER trial) [see Clinical Studies (14.4)], anti-liraglutide antibodies were detected in 11 out of the 1247 (0.9%) liraglutide-treated patients with antibody measurements. Of the 11 liraglutide-treated patients who developed anti-liraglutide antibodies, none were observed to develop neutralizing antibodies to liraglutide, and 5 patients (0.4%) developed cross-reacting antibodies against native GLP-1.

TRESIBA (insulin degludec)

In a 52-week study of adult insulin-naïve type 2 diabetes mellitus patients, of the patients who received insulin degludec, 13/760 (2%) patients were positive at baseline for anti-insulin degludec antibodies and 46/744 (6%) patients developed anti-insulin degludec antibodies at least once during the study. The 58/60 (97%) patients who were positive for anti-insulin degludec antibodies were also positive for anti-human insulin antibodies.

13 NONCLINICAL TOXICOLOGY

13.1 Carcinogenesis, Mutagenesis, Impairment of Fertility

XULTOPHY 100/3.6

No studies have been conducted with the XULTOPHY 100/3.6 combination to evaluate carcinogenesis, mutagenesis or impairment of fertility. The following data are based upon studies with insulin degludec and liraglutide individually.

Insulin degludec

Standard 2-year carcinogenicity studies in animals have not been performed to evaluate the carcinogenic potential of insulin degludec.

In a 52-week study including human insulin (NPH insulin) as comparator, Sprague-Dawley rats were dosed subcutaneously with insulin degludec at 3.3, 6.7, and 10 U/kg/day, resulting in 5 times the human exposure (AUC) when compared to a human subcutaneous dose of 0.75 U/kg/day. Human insulin was dosed at 6.7 U/kg/day. No treatment-related increases in incidences of hyperplasia, benign or malignant tumors were recorded in female mammary glands from rats dosed with insulin degludec and no treatment related changes in the female mammary gland cell proliferation were found using BrdU incorporation. Further, no treatment related changes in the occurrence of hyperplastic or neoplastic lesions were seen in any animals dosed with insulin degludec when compared to vehicle or human insulin.

Genotoxicity testing of insulin degludec was not performed.

In a combined fertility and embryo-fetal study in male and female rats, treatment with insulin degludec up to 21 U/kg/day (approximately 5 times the human subcutaneous dose of 0.75 U/kg/day, based on U/body surface area) prior to mating and in female rats during gestation had no effect on mating performance and fertility.

Liraglutide

A 104-week carcinogenicity study was conducted in male and female CD-1 mice at doses of 0.03, 0.2, 1.0, and 3.0 mg/kg/day liraglutide administered by bolus subcutaneous injection yielding systemic exposures 0.2-, 2-, 10- and 45-times the human exposure, respectively, at the MRHD of 1.8 mg/day based on plasma AUC comparison. A dose-related increase in benign thyroid C-cell adenomas was seen in the 1.0 and the 3.0 mg/kg/day groups with incidences of 13% and 19% in males and 6% and 20% in females, respectively. C-cell adenomas did not occur in control groups or 0.03 and 0.2 mg/kg/day groups. Treatment-related malignant C-cell carcinomas occurred in 3% of females in the 3.0 mg/kg/day group. Thyroid C-cell tumors are rare findings during carcinogenicity testing in mice. A treatment-related increase in fibrosarcomas was seen on the dorsal skin and subcutis, the body surface used for drug injection, in males in the 3 mg/kg/day group. These fibrosarcomas were attributed to the high local concentration of drug near the injection site. The liraglutide concentration in the clinical formulation (6 mg/mL) is 10-times higher than the concentration in the formulation used to administer 3 mg/kg/day liraglutide to mice in the carcinogenicity study (0.6 mg/mL).

A 104-week carcinogenicity study was conducted in male and female Sprague Dawley rats at doses of 0.075, 0.25 and 0.75 mg/kg/day liraglutide administered by bolus subcutaneous injection with exposures 0.5-, 2- and 8-times the human exposure, respectively, resulting from the MRHD based on plasma AUC comparison. A treatment-related increase in benign thyroid C-cell adenomas was seen in males in 0.25 and 0.75 mg/kg/day liraglutide groups with incidences of 12%, 16%, 42%, and 46% and in all female liraglutide-treated groups with incidences of 10%, 27%, 33%, and 56% in 0 (control), 0.075, 0.25, and 0.75 mg/kg/day groups, respectively. A treatment-related increase in malignant thyroid C-cell carcinomas was observed in all male liraglutide-treated groups with incidences of 2%, 8%, 6%, and 14% and in females at 0.25 and 0.75 mg/kg/day with incidences of 0%, 0%, 4%, and 6% in 0 (control), 0.075, 0.25, and 0.75 mg/kg/day groups, respectively. Thyroid C-cell carcinomas are rare findings during carcinogenicity testing in rats.

Studies in mice demonstrated that liraglutide-induced C-cell proliferation was dependent on the GLP-1 receptor and that liraglutide did not cause activation of the REarranged during Transfection (RET) proto-oncogene in thyroid C-cells.

Human relevance of thyroid C-cell tumors in mice and rats is unknown and has not been determined by clinical studies or nonclinical studies [see Boxed Warning, Warnings, Precautions (5.1)].

Liraglutide was negative with and without metabolic activation in the Ames test for mutagenicity and in a human peripheral blood lymphocyte chromosome aberration test for clastogenicity. Liraglutide was negative in repeat-dose in vivo micronucleus tests in rats.

In rat fertility studies using subcutaneous doses of 0.1, 0.25 and 1 mg/kg/day liraglutide, males were treated for 4 weeks prior to and throughout mating and females were treated 2 weeks prior to and throughout mating until gestation day 17. No direct adverse effects on male fertility was observed at doses up to 1 mg/kg/day, a high dose yielding an estimated systemic exposure 11- times the human exposure at the MRHD, based on plasma AUC. In female rats, an increase in early embryonic deaths occurred at 1 mg/kg/day. Reduced body weight gain and food consumption were observed in females at the 1 mg/kg/day dose.

14 CLINICAL STUDIES

14.1 Overview of Clinical Studies

A total of 3908 patients with type 2 diabetes mellitus participated in 6 randomized, parallel and active or placebo-controlled phase 3 trials of 26 weeks duration.

Three studies were conducted in patients inadequately controlled on one or more OADs (e.g. metformin, pioglitazone, sulfonylurea, or sodium-glucose cotransporter-2 inhibitors (SGLT2i) (Tables 5-7). Three studies were conducted in patients converting from liraglutide or basal insulin: one study was conducted in patients converting from liraglutide (with doses up to 1.8 mg), (Table 8), one study was conducted in patients converting from any basal insulin (Table 9), and one study was conducted in patients converting from insulin glargine U-100 (Table 10).

In all trials, XULTOPHY 100/3.6 was titrated twice weekly by increments or decrements of 2 units (2 units insulin degludec/0.072 mg liraglutide), towards a pre-specified fasting blood glucose target. The same titration algorithm was applied for basal insulin comparators.

14.2 Patients with Type 2 Diabetes Mellitus Uncontrolled on OAD Treatment

NCT01336023: The efficacy and safety of XULTOPHY 100/3.6 compared to insulin degludec and liraglutide, all administered once-daily, was studied in a 26-week randomized, open-label, three-arm parallel trial in 1,660 patients with type 2 diabetes mellitus inadequately controlled on 1-2 OADs (metformin or metformin with or without pioglitazone).

The mean age of the trial population was 55 years and mean duration of diabetes was 7 years. 51% were male. 62% were White, 7% were Black or African American and 15% were Hispanic or Latino ethnicity, 5% of patients had eGFR <60 mL/min/1.73 m^2; no patients had eGFR <30 mL/min/1.73 m^2. The mean BMI was 31.2 kg/m^2.

The starting dose of XULTOPHY 100/3.6 was 10 units (10 units insulin degludec/0.36 mg liraglutide). The starting dose of insulin degludec was 10 units. XULTOPHY 100/3.6 and insulin degludec were titrated twice weekly towards a target fasting blood glucose goal of 72 to 90 mg/dL. Patients in the liraglutide arm followed a fixed dose escalation scheme with a starting dose of 0.6 mg and a dose increase of 0.6 mg weekly until a daily dose of 1.8 mg was reached. Patients continued on pre-trial treatment with metformin or metformin and pioglitazone throughout the trial.

At the end of 26 weeks, treatment with XULTOPHY 100/3.6, insulin degludec, and liraglutide resulted in a reduction in HbA1c from baseline of 1.81%, 1.35% and 1.21%, respectively, (see Table 5). The end of trial dose of XULTOPHY 100/3.6 was 38 units (38 units insulin degludec/1.37 mg liraglutide).

Table 5. Results of a 26-Week Trial with XULTOPHY 100/3.6 in Patients with Type 2 Diabetes Mellitus Inadequately Controlled on Metformin Alone or in Combination with Pioglitazone

 | XULTOPHY 100/3.6 + metformin ± pioglitazone | Insulin degludec + metformin ± pioglitazone | Liraglutide + metformin ± pioglitazone
Total (N) | 833 | 413 | 414
HbA1c (%)
Baseline | 8.3 | 8.3 | 8.3
End of Trial (LS Mean)# | 6.5 | 6.9 | 7.1
Change from baseline (LS Mean)# | -1.81 | -1.35 | -1.21
Estimated treatment difference [95% CI]# | -- | -0.46% [-0.59; -0.34]A | -0.6% [-0.72; -0.47]A
Percentage of patients achieving HbA1c <7%## | 74.1% | 60.5% | 56%
Fasting Plasma Glucose (FPG) (mg/dL)
Baseline | 166 | 169 | 163
End of Trial (LS Mean)# | 104 | 107 | 133
Change from baseline (LS Mean)# | -61.8 | -59.2 | -32.4

A p<0.01. Primary endpoint was tested for non-inferiority of XULTOPHY 100/3.6 to insulin degludec based on pre-specified non-inferiority margin of 0.3% and for superiority of XULTOPHY 100/3.6 to liraglutide.

# Estimated using an ANCOVA with treatment, baseline HbA1c stratum, sub-study, concomitant diabetes treatment and country as factors and baseline response as covariate. Multiple imputation modeled “return to baseline” of the treatment effect for subjects having missing week 26 data.

## Patients with missing HbA1c value at week 26 data were considered non-responders.

There were 11.8% of subjects in the XULTOPHY 100/3.6 arm, 12.3% in the insulin degludec arm and 15.5% in the liraglutide arm for whom HbA1c data was missing at week 26.

NCT01618162: The efficacy and safety of XULTOPHY 100/3.6 compared to placebo were studied in a 26-week randomized, double-blind, treat-to-target trial in 435 patients with type 2 diabetes mellitus inadequately controlled on sulfonylurea alone or in combination with metformin.

The mean age of the trial population was 60 years, and mean duration of diabetes was 9 years. 52% were male. 75% were White, 7% were Black or African American and 9% were Hispanic or Latino ethnicity, 11% of patients had eGFR < 60 mL/min/1.73 m^2; no patients had eGFR <30 mL/min/1.73 m^2. The mean BMI was 31.5 kg/m^2.

XULTOPHY 100/3.6 was started at 10 units (10 units insulin degludec/0.36 mg liraglutide) and titrated twice weekly towards a target fasting blood glucose goal of 72 to108 mg/dL. Patients continued on pre-trial treatment with sulfonylurea, with or without metformin throughout the trial.

Treatment with XULTOPHY 100/3.6 for 26 weeks resulted in a statistically significant reduction in mean HbA1c compared to placebo (see Table 6). The end of trial dose of XULTOPHY 100/3.6 was 28 units (28 units insulin degludec/1.01 mg liraglutide).

Table 6. Results of a 26-Week Trial with XULTOPHY 100/3.6 in Patients with Type 2 Diabetes Mellitus Inadequately Controlled on Sulfonylurea Alone or in Combination with Metformin

 | XULTOPHY 100/3.6; + sulfonylurea###; ± metformin | Placebo; + sulfonylurea###; ± metformin
Total (N) | 289 | 146
HbA1c (%)
Baseline | 7.9 | 7.9
End of Trial (LS Mean)# | 6.5 | 7.3
Change from baseline (LS Mean)# | -1.42 | -0.62
Estimated treatment difference [95% CI]# | -0.81% [-0.98; -0.63]A
Percentage of patients achieving HbA1c <7%## | 70.9% | 26.7%
FPG (mg/dL)
Baseline | 164 | 165
End of Trial (LS Mean)# | 118 | 152
Change from baseline (LS Mean)# | -46.2 | -12.1

A p<0.01. Primary endpoint was tested for superiority of XULTOPHY 100/3.6 to placebo.

# Estimated using an ANCOVA with treatment, region and pre-trial medication as fixed factors and baseline response as covariate. Multiple imputation modeled “jump-to-control” of the treatment effect for subjects having missing week 26 data.

## Patients with missing HbA1c value at week 26 data were considered non-responders.

There were 12.8% of subjects in the XULTOPHY 100/3.6 arm and 24.7% in the placebo arm for whom HbA1c data was missing at week 26.

### Dose of sulfonylurea was ≥ half of the maximum approved dose.

NCT02773368: The efficacy and safety of XULTOPHY 100/3.6 compared to insulin glargine U-100, both administered once-daily, were studied in a 26-week randomized, open-label, two-arm parallel trial in 420 patients with type 2 diabetes mellitus inadequately controlled on a SGLT2i alone or in combination with other OADs [with or without metformin, pioglitazone, and/or dipeptidyl peptidase-4 9DPP-4) inhibitor]. At randomization, the DPP-4 inhibitor was discontinued.

The mean age of the trial population was 57 years and mean duration of diabetes was 10 years. 59% were male. 82% were White, 1% were Black or African American and 16% were Hispanic or Latino ethnicity, 3% of patients had eGFR <60 mL/min/1.73 m^2; none of the patients had eGFR <30 mL/min/1.73 m^2. The mean BMI was 31.2 kg/m^2.

The starting dose of XULTOPHY 100/3.6 was 10 units (10 units insulin degludec/0.36 mg liraglutide). The starting dose of insulin glargine U-100 was 10 units. XULTOPHY 100/3.6 and insulin glargine U-100 were titrated twice weekly to target a fasting blood glucose goal of 72 to 90 mg/dL. Patients could not increase the dose of XULTOPHY 100/3.6 and insulin glargine U-100 by more than 4 units per week, and there was no maximum allowed dose of insulin glargine. The patients continued on pretrial treatment with SGLT2i, with or without other OADs throughout the entire trial. The targeted fasting blood glucose goal was achieved by 49% of patients randomized to XULTOPHY 100/3.6 and 41.9% of patients randomized to insulin glargine at 26 weeks.

At the end of 26 weeks, XULTOPHY 100/3.6 resulted in a reduction in HbA1c from baseline of 1.97% and insulin glargine U-100 resulted in a reduction of 1.59% (see Table 7). At the end of trial, the average dose of XULTOPHY 100/3.6 was 36 units (36 units insulin degludec/1.3 mg liraglutide) and the dose of insulin glargine was 54 units; it is unclear that these observed differences in insulin doses are clinically important. The difference in HbA1c effect observed at 26 weeks may not necessarily reflect the effect in the care setting where insulin glargine may be more rapidly titrated.

Table 7. Results of a 26-Week Trial in Patients with Type 2 Diabetes Mellitus Inadequately

Controlled on SGLT2i Alone or in Combination with Metformin, Pioglitazone and/or DPP4 Inhibitor

 | XULTOPHY 100/3.6; + SGLT2i; ± metformin± pioglitazone | Insulin Glargine U-100; + SGLT2i; ± metformin± pioglitazone
Total (N) | 210 | 210
HbA1c (%)
Baseline | 8.2 | 8.4
End of Trial (LS Mean)# | 6.3 | 6.7
Change from baseline (LS Mean)# | -1.97 | -1.59
Estimated treatment difference [95% CI]# | -0.38% [-0.54; -0.23]A
Percentage of patients achieving HbA1c <7%## | 79.5% | 68.6%
FPG (mg/dL)
Baseline | 171 | 172
End of Trial (LS Mean)### | 108 | 112
Change from baseline (LS Mean)### | -63.8 | -59.9

A Primary endpoint was tested for non-inferiority of XULTOPHY 100/3.6 to insulin glargine U-100 on a non-inferiority margin of 0.3%.

# Estimated using an ANCOVA with treatment, pretrial OAD group and region as factors and corresponding baseline value as covariate. For HbA1c (%), missing week 26 measurements from subjects who discontinued early were multiply-imputed using information from subjects who also discontinued early but still had a week 26 measurement (retrieved dropouts).

## Patients with missing HbA1c value at week 26 data were considered non-responders.

There were 6.2% of subjects in the XULTOPHY 100/3.6 arm and 2.4% in the insulin glargine U-100 arm for whom HbA1c data was missing at week 26.

### Missing week 26 FPG measurements from subjects who discontinued early were imputed using multiple imputation with a mean for each subject equal to their respective baseline value.

14.3 Patients Currently on Basal Insulin or GLP-1 Receptor Agonist

Converting to XULTOPHY 100/3.6 from GLP-1 receptor agonist

NCT01676116: The efficacy and safety of XULTOPHY 100/3.6 (once-daily) compared to unchanged pretrial liraglutide up to a dose of 1.8 mg daily, were studied in a 26-week randomized, open-label, treat-to-target (fasting blood glucose goal of 72 to 90 mg/dL) trial. The trial included 348 patients with type 2 diabetes mellitus inadequately controlled on liraglutide and metformin alone or in combination with pioglitazone, sulfonylurea or both. Oral anti-diabetic drugs (OADs) were continued at pretrial doses throughout the trial, and 22% of subjects were treated with sulfonylureas (SU) in combination with metformin with or without pioglitazone. The mean age of the population was 58 years, and mean duration of diabetes was 10 years. 49% were male. 91% were White, 8% Black or African American. 11% were Hispanic or Latino ethnicity, 6% of patients had eGFR <60 mL/min/1.73 m^2; no patient had eGFR <30 mL/min/1.73 m^2. The mean BMI was 33.1 kg/m^2.

The starting dose of XULTOPHY 100/3.6 was 16 units (16 units insulin degludec/0.58 mg liraglutide), and the average starting dose of liraglutide was 1.7 mg. XULTOPHY 100/3.6 was titrated twice weekly to target a fasting blood glucose goal of 72 to 90 mg/dL. The end of trial dose of XULTOPHY 100/3.6 was 44 units (44 units insulin degludec/1.58 mg liraglutide). The primary endpoint, change in HbA1c, was tested for superiority of XULTOPHY 100/3.6 to unchanged liraglutide therapy.

At the end of 26 weeks, there was a reduction in HbA1c from baseline of 1.31% for XULTOPHY 100/3.6 and 0.36% for liraglutide (see Table 8).

Table 8. Results of a 26-Week Trial with XULTOPHY 100/3.6 in Patients with Type 2 Diabetes Mellitus Inadequately Controlled on Liraglutide up to 1.8 mg Daily

 | XULTOPHY 100/3.6 + metformin±pioglitazone±SU | liraglutide 1.8 mg+ metformin±pioglitazone±SU
Total (N) | 232 | 116
HbA1c (%)
Baseline | 7.8 | 7.8
End of Trial (LS Mean)# | 6.4 | 7.4
Change from baseline (LS Mean)# | -1.31 | -0.36
Estimated treatment difference [95% CI] | -0.95 [-1.15; -0.75]A
Percentage of patients achieving HbA1c <7%## | 74.6% | 30.2%
FPG (mg/dL)
Baseline | 161 | 169
End of Trial (LS Mean)# | 112 | 153
Change from baseline (LS Mean)# | -51.1 | -10.9

A Test for superiority evaluated at 5.0% level for significance, (p<0.0001)
# Estimated using an ANCOVA with treatment, pretrial liraglutide and region as fixed factors and baseline response as covariate. Multiple imputation modeled “return to baseline” of the treatment effect for subjects having missing week 26 data.
## Patients with missing HbA1c data at week 26 were considered as non-responders.
There were 5.2% of subjects in the XULTOPHY 100/3.6 arm and 19m% in the liraglutide arm for whom HbA1c data was missing at week 26.

Figure 3. Mean HbA1c (%) By Treatment Week in Patients with Type 2 Diabetes Mellitus Inadequately Controlled on Liraglutide

IDegLira=XULTOPHY 100/3.6

Converting from basal insulin

NCT01392573: The efficacy and safety of XULTOPHY 100/3.6 compared to insulin degludec, both once-daily and added on to metformin, were studied in a 26-week randomized, double-blind, trial in 398 patients with type 2 diabetes mellitus inadequately controlled on basal insulin and metformin alone or in combination with sulfonylurea/glinides. Basal insulin and sulfonylurea/glinides were discontinued at randomization.

The mean age of the trial population was 57 years, and mean duration of diabetes was 11 years. 55% were male. 77% were White, 5% Black or African American. 10% were Hispanic or Latino ethnicity, 7% of patients had eGFR < 60 mL/min/1.73 m^2; no patient had eGFR <30 mL/min/1.73 m^2. The mean BMI was 33.7 kg/m^2. The mean dose of metformin and basal insulin in patients entering the trial was approximately 2 g and 29 units, respectively.

The starting dose of XULTOPHY 100/3.6 and insulin degludec was 16 units (16 units insulin degludec/0.58 mg liraglutide) and 16 units, respectively. XULTOPHY 100/3.6 and degludec were to be titrated twice weekly to target a fasting blood glucose goal of 72 to 90 mg/dL. Patients could not increase their dose by more than 4 units per week, and the maximum dose of insulin degludec was limited to 50 units. The targeted fasting blood glucose goal was achieved in 24% of patients randomized to insulin degludec and in 31.6% of the patients randomized to XULTOPHY 100/3.6 at 26 weeks.

At the end of 26 weeks, reductions in HbA1c from baseline of 1.94% for XULTOPHY 100/3.6 and 1.05% for insulin degludec limited to 50 units daily were observed (see Table 9). The mean difference (95% CI) in HbA1c reduction between XULTOPHY 100/3.6 and insulin degludec was -0.89 [-1.10; -0.68] and statistically significant. The trial was designed to show the contribution of the liraglutide component to glycemic lowering and the insulin degludec dosing algorithm was selected to isolate the effect of the GLP-1 component. At the end of the trial, the doses of insulin degludec were equivalent between treatment groups. The mean final dose of XULTOPHY 100/3.6 and insulin degludec was 46 units (for XULTOPHY 100/3.6: 46 units insulin degludec/1.66 mg liraglutide). The difference in glucose lowering effect observed in the trial may not necessarily reflect the effect that will be observed in the care setting where insulin degludec dosage can be different than that used in the trial.

Table 9. Results of a 26-Week Trial in Patients with Type 2 Diabetes Mellitus Inadequately Controlled on Basal Insulin

 | XULTOPHY 100/3.6 + metformin | Insulin degludec* + metformin
Total (N) | 199 | 199
HbA1c (%)
Baseline | 8.7 | 8.8
End of Trial (LS Mean)# | 6.9 | 7.7
Change from baseline (LS Mean)# | -1.94 | -1.05
Estimated treatment difference [95% CI]# | -0.89 [-1.10; -0.68]A
Percentage of patients achieving HbA1c <7%## | 57.3% | 22.6%
FPG (mg/dL)
Baseline | 175 | 172
End of Trial (LS Mean)# | 110 | 118
Change from baseline (LS Mean)# | -63.5 | -55.5

A p<0.01. The trial was designed to show the contribution of the liraglutide component to glycemic lowering and the insulin degludec dosing algorithm was selected to isolate the effect of the GLP-1 component. At the end of the trial, the doses of insulin degludec were equivalent between treatment groups. The mean final dose of XULTOPHY 100/3.6 and insulin degludec was 46 units (for XULTOPHY 100/3.6: 46 units insulin degludec/1.66 mg liraglutide). The difference in glucose lowering effect observed in the trial may not necessarily reflect the effect that will be observed in the care setting where alternative insulin degludec dosage can be used.

* Maximum dose 50 units

# Estimated using an ANCOVA with treatment, country, and previous antidiabetic treatment as fixed factors and baseline response as covariate. Multiple imputation modeled “jump to control” of the treatment effect for subjects having missing week 26 data.
## Patients with missing HbA1c data at week 26 were considered non-responders.

There were 11.1% of subjects in the XULTOPHY 100/3.6 arm and 13.1% in the insulin degludec arm for whom HbA1c data was

missing at week 26.

NCT01952145: The efficacy and safety of XULTOPHY 100/3.6 compared to insulin glargine U-100, both once-daily and added on to metformin, were studied in a 26-week randomized, open-label, two-arm parallel trial in 557 patients with type 2 diabetes mellitus inadequately controlled on insulin glargine U-100 and metformin.

The mean age of the trial population was 59 years and mean duration of diabetes was 12 years. 50% were male. 95% were White, 2% Black or African American. 43% were Hispanic or Latino ethnicity, 6% of patients had eGFR < 60mL/min/1.73m^2; one patient had eGFR < 30mL/min/1.73m^2. The mean BMI was 32 kg/m^2. The mean dose of insulin glargine U-100 in patients entering the trial was 32 units.

XULTOPHY 100/3.6 and insulin glargine were to be titrated twice weekly to target a fasting blood glucose goal of 72 to 90 mg/dL. The starting dose of XULTOPHY 100/3.6 was 16 units (16 units insulin degludec/0.58 mg liraglutide). The average starting dose of insulin glargine U-100 was 32 units. Patients could not increase the dose of the two products by more than 4 units per week and there was no maximum allowed dose of insulin glargine. The targeted fasting plasma blood glucose goal was achieved in 39.6% of patients randomized to insulin glargine and 32.9% of the patients randomized to XULTOPHY 100/3.6 at 26 weeks.

At the end of 26 weeks, treatment with XULTOPHY 100/3.6 resulted in a reduction in HbA1c from baseline of 1.67% and was 1.16% for insulin glargine U-100 (see Table 10) and excluded the pre-specified non-inferiority margin of 0.3%. At the end of the trial, the average dose of XULTOPHY 100/3.6 was 41 units (41 units insulin degludec/1.48 mg liraglutide) and the dose of glargine was 66 units, it is unclear that these observed differences in insulin doses are clinically important. The difference in HbA1c effect observed at 26 weeks may not necessarily reflect the effect in the care setting where insulin glargine may be more rapidly titrated.

Table 10. Results of a 26-Week Trial in Patients with Type 2 Diabetes Mellitus Inadequately Controlled on Insulin Glargine U-100

 | XULTOPHY 100/3.6; + metformin | Insulin glargine U-100; + metformin
Total (N) | 278 | 279
HbA1c (%)
Baseline | 8.4 | 8.2
End of Trial (LS Mean)# | 6.6 | 7.1
Change from baseline (LS Mean)# | -1.67 | -1.16
Estimated treatment difference [95% CI] | -0.51 [-0.67; -0.34] A
Percentage of patients achieving HbA1c <7%## | 68.3% | 46.2%
FPG (mg/dL)
Baseline | 161 | 160
End of Trial (LS Mean)# | 110 | 110
Change from baseline (LS Mean)# | -49.9 | -49.6

A p<0.01. Primary endpoint was tested for noninferiority of XULTOPHY 100/3.6 to insulin glargine U-100. The difference in glucose lowering effect observed in the trial may not necessarily reflect the effect that will be observed in the care setting where alternative insulin glargine dosage can be used.
# Estimated using an ANCOVA with treatment and region as fixed factors and baseline response as covariate. Multiple imputation modeled “return to baseline” of the treatment effect for subjects having missing week 26 data.
## Patients with missing HbA1c value at week 26 data were considered non-responder.
There were 10.1% of subjects in the XULTOPHY 100/3.6 arm and 4.7% in the insulin glargine U-100 arm for whom HbA1c data was missing at week 26.

14.4 Cardiovascular Outcomes Trials in Patients with Type 2 Diabetes Mellitus and Atherosclerotic Cardiovascular Disease Conducted with Liraglutide 1.8 mg and Insulin Degludec

The effect of XULTOPHY 100/3.6 on the risk of cardiovascular outcomes in patients with type 2 diabetes mellitus and atherosclerotic cardiovascular disease has not been established. The studies below were conducted with liraglutide 1.8 mg and insulin degludec, individually.

Liraglutide 1.8 mg

The LEADER trial (NCT01179048) randomized 9,340 patients with inadequately controlled type 2 diabetes mellitus and cardiovascular disease to liraglutide 1.8 mg or placebo in addition to standard of care treatments for type 2 diabetes mellitus for a median follow up of 3.5 years.

Patients either were 50 years of age or older with established, stable cardiovascular, cerebrovascular, peripheral artery disease, chronic kidney disease or chronic heart failure (80% of patients) or were 60 years of age or older and had other specified risk factors for cardiovascular disease (20% of patients). The population was 64% male, 78% White, 10% Asian, and 8% Black or African American; 12% of the population was Hispanic or Latino. The mean duration of type 2 diabetes mellitus was 13 years, the mean HbA1c was 8.7% and the mean BMI was 33 kg/m^2; the mean eGFR at baseline was 79 mL/min/1.73 m^2.

In total, 96.8% of the patients completed the trial; vital status was available for 99.7%. The primary endpoint was the time from randomization to first occurrence of a major adverse cardiovascular event (MACE) defined as: cardiovascular death, non-fatal myocardial infarction, or non-fatal stroke. No increased risk for MACE was observed with liraglutide 1.8 mg. The total number of primary component MACE endpoints was 1302 (608[13.0%] with liraglutide 1.8 mg and 694 [14.9%] with placebo).

Insulin degludec

The DEVOTE trial (NCT01959529) randomized 7,637 patients with inadequately controlled type 2 diabetes mellitus and cardiovascular disease to either insulin degludec or insulin glargine U-100. Each was administered once-daily in addition to standard of care treatments for diabetes for a median duration of follow up of 2 years.

Patients either were 50 years of age or older and had established, stable cardiovascular, cerebrovascular, peripheral artery disease, chronic kidney disease or chronic heart failure (85% of patients) or were 60 years of age or older and had other specified risk factors for cardiovascular disease (15% of patients). The population was 63% male, 76% White 11% Black or African American, and 10% Asian; 15% of the population was Hispanic or Latino. The mean HbA1c was 8.4% and the mean BMI was 33.6 kg/m^2. The baseline mean eGFR was 68 mL/min/1.73m^2.

In total, 98% of the patients completed the trial; vital status was known at the end of the trial for 99%. The primary endpoint was the time from randomization to the first occurrence of MACE, defined as: cardiovascular death, non-fatal myocardial infarction, or non-fatal stroke. No increased risk for MACE was observed with insulin degludec when compared to insulin glargine U-100. The total number of primary MACE endpoints was 681 (325 [8.5%] with insulin degludec and 356 [9.3%] with insulin glargine).

16 HOW SUPPLIED/STORAGE AND HANDLING

How Supplied

XULTOPHY 100/3.6 (insulin degludec and liraglutide) injection is an injection supplied as a clear, colorless solution in a 3 mL prefilled, disposable, single-patient-use pen injector. The XULTOPHY 100/3.6 pen dials in one-unit increments.

Dosage Unit/Strength | Package size | NDC #
3 mL single-patient-use XULTOPHY 100/3.6 pen (100 units/mL insulin degludec and 3.6 mg/mL liraglutide) | Package of 5 | 0169-2911-15

Recommended Storage

Dispense in the original sealed carton with the enclosed Instructions for Use.

Prior to first use, XULTOPHY 100/3.6 should be stored between 36°F to 46°F (2°C and 8°C) until the expiration date printed on the label. Store prefilled pens in the carton so they will stay clean and protected from light. Do not store in the freezer or directly adjacent to the refrigerator cooling element. Do not freeze. Do not use XULTOPHY 100/3.6 if it has been frozen.

After first use, the XULTOPHY 100/3.6 pen can be stored for 21 days at controlled room temperature 59°F to 86°F (15°C to 30°C) or in a refrigerator 36°F to 46°F (2°C to 8°C). Keep all XULTOPHY 100/3.6 pens away from direct heat and light.

Always remove the needle after each injection and store the XULTOPHY 100/3.6 pen without a needle attached. This prevents contamination and/or infection, or leakage of the XULTOPHY 100/3.6 pen, and will ensure accurate dosing. Always use a new needle for each injection to prevent contamination.

The storage conditions are summarized in Table 11:

Table 11. Storage Conditions for XULTOPHY 100/3.6 Pen

Prior to first use | After first use
Refrigerated 36°F to 46°F (2°C to 8°C) | Room Temperature 59°F to 86°F (15°C to 30°C) | Refrigerated 36°F to 46°F (2°C to 8°C)
Until expiration date | 21 Days

17 PATIENT COUNSELING INFORMATION

Advise the patient to read the FDA-approved patient labeling (Medication Guide and Instructions for Use)

Risk of Thyroid C-cell Tumors

Inform patients that liraglutide, one of the components of XULTOPHY 100/3.6, causes benign and malignant thyroid C-cell tumors in mice and rats and that the human relevance of this finding is unknown. Counsel patients to report symptoms of thyroid tumors (e.g., a lump in the neck, hoarseness, dysphagia or dyspnea) to their physician [see Boxed Warning, Warnings and Precautions (5.1)].

Acute Pancreatitis

Inform patients of the potential risk for pancreatitis acute pancreatitis and its symptoms: severe abdominal pain that may radiate to the back, and which may or may not be accompanied by nausea or vomiting. Instruct patients to discontinue XULTOPHY 100/3.6 promptly and contact their physician if pancreatitis is suspected [see Warnings and Precautions (5.2)].

Never Share a XULTOPHY 100/3.6 Pen Between Patients

Advise patients that they must never share a XULTOPHY 100/3.6 pen with another person, even if the needle is changed, because doing so carries a risk for transmission of blood-borne pathogens [see Warnings and Precautions (5.3].

Hyperglycemia or Hypoglycemia with Changes in Insulin Regimen

Inform patients that hypoglycemia is the most common adverse reaction with insulin products. Inform patients of the symptoms of hypoglycemia (e.g., impaired ability to concentrate and react). This may present a risk in situations where these abilities are especially important, such as driving or operating other machinery. Advise patients who have frequent hypoglycemia or reduced or absent warning signs of hypoglycemia to use caution when driving or operating machinery.

Advise patients that changes in insulin regimen can predispose to hyperglycemia or hypoglycemia and that changes in insulin regimen should be made under close medical supervision [see Warnings and Precautions (5.4)].

Overdose due to Medication Errors

Inform patients that XULTOPHY 100/3.6 contains two drugs: insulin degludec and liraglutide. Accidental mix-ups between insulin products have been reported. To avoid medication errors between XULTOPHY 100/3.6 (an insulin containing product) and other insulin products, instruct patients to always check the label before each injection.

Advise patients that the administration of more than 50 units of XULTOPHY 100/3.6 daily can result in overdose of the liraglutide component. Instruct patients not to administer concurrently with other glucagon-like peptide-1 receptor agonists [see Warnings and Precautions (5.5)].

Acute Kidney Injury Due to Volume Depletion

Inform patients of the potential risk of acute kidney injury due to dehydration associated with gastrointestinal adverse reactions. Advise patients to take precautions to avoid fluid depletion. Inform patients of the signs and symptoms of acute kidney injury and instruct them to promptly report any of these signs or symptoms or persistent (or extended) nausea, vomiting, and diarrhea to their healthcare provider [see Warnings and Precautions (5.7)].

Severe Gastrointestinal Adverse Reactions

Inform patients of the potential risk of severe gastrointestinal adverse reactions. Instruct patients to contact their healthcare provider if they have severe or persistent gastrointestinal symptoms [see Warnings and Precautions (5.8)].

Hypersensitivity Reactions

Inform patients that serious hypersensitivity reactions have been reported during postmarketing use of liraglutide, one of the components of XULTOPHY 100/3.6.

Advise patients on the symptoms of hypersensitivity reactions and instruct them must stop taking XULTOPHY 100/3.6 and seek medical advice promptly [see Warnings and Precautions (5.9)].

Acute Gallbladder Disease

Inform patients of the potential risk for cholelithiasis or cholecystitis. Instruct patients to contact their physician if cholelithiasis or cholecystitis is suspected for appropriate clinical follow-up [see Warnings and Precautions (5.10)].

Pulmonary Aspiration During General Anesthesia or Deep Sedation

Inform patients that XULTOPHY 100/3.6 may cause their stomach to empty more slowly which may lead to complications with anesthesia or deep sedation during planned surgeries or procedures. Instruct patients to inform healthcare providers prior to any planned surgeries or procedures if they are taking XULTOPHY 100/3.6 [see Warnings and Precautions (5.13)].

Pregnancy

Advise a pregnant woman of the potential risk to a fetus. Advise women to inform their healthcare provider if they are pregnant or intend to become pregnant [see Use in Specific Populations (8.1)].

Missed Dose

Inform patients not to take an extra dose of XULTOPHY 100/3.6 or increase the dose to make up for the missed dose. Instruct patients who miss a dose of XULTOPHY 100/3.6 to resume the once-daily dosage regimen as prescribed with the next scheduled dose. If more than three days have elapsed since the last XULTOPHY 100/3.6 dose, reinitiate XULTOPHY 100/3.6 at the recommended starting dose to reduce the risk of gastrointestinal adverse reactions associated with reinitiation of treatment. XULTOPHY 100/3.6 should be titrated at the direction of a healthcare provider [see Dosage and Administration (2.1, 2.2, 2.3, 2.4)].

© 2025 Novo Nordisk

Novo Nordisk®, TRESIBA® and XULTOPHY® 100/3.6 are registered trademarks of Novo Nordisk A/S.

PATENT Information: http://novonordisk-us.com/products/product-patents.html

Manufactured by:

Novo Nordisk Inc.

800 Scudders Mill Road

Plainsboro, NJ 08536

U.S. License Number 1261

For information about XULTOPHY 100/3.6 contact:

Novo Nordisk Inc.

800 Scudders Mill Road

Plainsboro, NJ 08536

1-800-727-6500 (Se habla español)

www.novonordisk-us.com

Medication Guide

XULTOPHY® 100/3.6 (ZUL-to-fye)
(insulin degludec and liraglutide) Injection, for subcutaneous injection

Read this Medication Guide before you start using XULTOPHY 100/3.6 and each time you get a refill. There may be new information. This information does not take the place of talking to your healthcare provider about your medical condition or your treatment.

What is the most important information I should know about XULTOPHY 100/3.6?

XULTOPHY 100/3.6 may cause serious side effects, including:

- Possible thyroid tumors, including cancer. Tell your healthcare provider if you get a lump or swelling in your neck, hoarseness, trouble swallowing, or shortness of breath. These may be symptoms of thyroid cancer. In studies with rats and mice, liraglutide, one of the components of XULTOPHY 100/3.6, and medicines that work like liraglutide caused thyroid tumors, including thyroid cancer. It is not known if XULTOPHY 100/3.6 will cause thyroid tumors or a type of thyroid cancer called medullary thyroid carcinoma (MTC) in people.
- Do not use XULTOPHY 100/3.6 if you or any of your family have ever had a type of thyroid cancer called medullary thyroid carcinoma (MTC), or if you have an endocrine system condition called Multiple Endocrine Neoplasia syndrome type 2 (MEN 2).

What is XULTOPHY 100/3.6?

- XULTOPHY 100/3.6 is an injectable prescription medicine that contains 2 diabetes medicines, insulin degludec, 100 units/mL, and liraglutide, 3.6 mg/mL. XULTOPHY 100/3.6 should be used along with diet and exercise to lower blood sugar (glucose) in adults with type 2 diabetes mellitus.
- XULTOPHY 100/3.6 is not recommended as the first choice of medicine for treating diabetes.
- XULTOPHY 100/3.6 is not recommended for use in combination with any other product containing liraglutide or another glucagon-like peptide 1 receptor agonist (GLP-1 receptor agonist).
- XULTOPHY 100/3.6 is not for use in people with type 1 diabetes or people with diabetic ketoacidosis (increased ketones in the blood or urine).
- It is not known if XULTOPHY 100/3.6 can be used with mealtime insulin.
- It is not known if XULTOPHY 100/3.6 is safe and effective for use in children.

Who should not use XULTOPHY 100/3.6?

Do not use XULTOPHY 100/3.6 if:

- you or any of your family have ever had a type of thyroid cancer called medullary thyroid carcinoma (MTC) or if you have an endocrine system condition called Multiple Endocrine Neoplasia syndrome type 2 (MEN 2).
- you are allergic to insulin degludec, liraglutide or any of the ingredients in XULTOPHY 100/3.6. See the end of this Medication Guide for a complete list of ingredients in XULTOPHY 100/3.6.
- you are having an episode of low blood sugar (hypoglycemia).

What should I tell my healthcare provider before using XULTOPHY 100/3.6?

Before using XULTOPHY 100/3.6, tell your healthcare provider about all your medical conditions, including if you:

- have or have had problems with your pancreas, kidneys, or liver.
- have heart failure or other heart problems. If you have heart failure, it may get worse while you take TZDs with XULTOPHY 100/3.6.
- have severe problems with your stomach, such as slowed emptying of your stomach (gastroparesis) or problems with digesting food.
- are taking certain medicines called GLP-1 receptor agonists.
- have had an allergic reaction to a GLP-1 receptor agonist medicine.
- are scheduled to have surgery or other procedures that use anesthesia or deep sleepiness (deep sedation).
- are pregnant or plan to become pregnant. It is not known if XULTOPHY 100/3.6 will harm your unborn baby. Tell your healthcare provider if you become pregnant or think you may be pregnant while using XULTOPHY 100/3.6.
- are breastfeeding or plan to breastfeed. It is not known if XULTOPHY 100/3.6 passes into your breast milk. Talk to your healthcare provider about the best way to feed your baby while using XULTOPHY 100/3.6.

Tell your healthcare provider about all the medicines you take, including prescription and over-the-counter medicines, vitamins, and herbal supplements. XULTOPHY 100/3.6 may affect the way some medicines work, and some medicines may affect the way XULTOPHY 100/3.6 works. Before using XULTOPHY 100/3.6, talk to your healthcare provider about low blood sugar and how to manage it. Tell your healthcare provider if you are taking other medicines to treat diabetes.

Know the medicines you take. Keep a list of them to show your healthcare provider and pharmacist when you get a new medicine.

How should I use XULTOPHY 100/3.6?

- Read the Instructions for Use that comes with XULTOPHY 100/3.6.
- Use XULTOPHY 100/3.6 exactly as your healthcare provider tells you to.
- Do not change your dosing schedule without first talking to your healthcare provider. The dose counter on your XULTOPHY 100/3.6 pen shows the number of units of XULTOPHY 100/3.6 to be injected.
- Your healthcare provider should show you how to use XULTOPHY 100/3.6 before you use it for the first time.
- XULTOPHY 100/3.6 is injected under the skin (subcutaneously) of your thigh, upper arm or stomach (abdomen).
- Do not inject XULTOPHY 100/3.6 into a vein (intravenously) or use in an insulin infusion pump.
- Use XULTOPHY 100/3.6 at the same time each day with or without food.
- If you miss a dose of XULTOPHY 100/3.6, resume your 1 time daily dosing schedule at the next scheduled dose. Do not take 2 doses at the same time or increase your dose to make up for the missed dose. If you miss more than 3 days of XULTOPHY 100/3.6, call your healthcare provider for further instructions about taking XULTOPHY 100/3.6 at the right dose and to help lower your chance of having an upset stomach.
- Do not dilute XULTOPHY 100/3.6 with any other liquids.
- Do not mix XULTOPHY 100/3.6 with any other insulin products or GLP-1 receptor agonists in the same injection.
- Do not split your dose of XULTOPHY 100/3.6. Give your full dose of XULTOPHY 100/3.6 in 1 injection.
- Check the Pen label each time you give your injection to make sure you are using the correct medicine.
- Do not take more than 50 units of XULTOPHY 100/3.6 each day. XULTOPHY 100/3.6 contains two medicines: insulin degludec and liraglutide. If you take too much XULTOPHY 100/3.6, it can cause severe nausea and vomiting. Do not take XULTOPHY 100/3.6 with other GLP-1 receptor agonists. If you take too much XULTOPHY 100/3.6, call your healthcare provider or go to the nearest hospital emergency room right away.
- Change (rotate) your injection sites within the area you choose with each injection to reduce your risk of getting lipodystrophy (pits in skin or thickened skin) and localized cutaneous amyloidosis (skin with lumps) at the injection sites.
  - Do not use the exact same spot for each injection.
  - Do not inject where the skin has pits, is thickened, or has lumps.
  - Do not inject where the skin is tender, bruised, scaly or hard, or into scars or damaged skin.
- Do not share your XULTOPHY 100/3.6 pen with other people, even if the needle has been changed. You may give other people a serious infection or get a serious infection from them.

Check your blood sugar levels. Ask your healthcare provider what your blood sugars should be and when you should check your blood sugar levels.

Your dose of XULTOPHY 100/3.6 and other diabetes medicines may need to change because of:

- change in level of physical activity or exercise, weight gain or loss, increased stress, illness, change in diet, or because of other medicines you take.

What should I avoid while taking XULTOPHY 100/3.6?

While taking XULTOPHY 100/3.6 do not:

- drive or operate heavy machinery, until you know how XULTOPHY 100/3.6 affects you.
- drink alcohol or use prescription or over-the-counter medicines that contain alcohol.

What are the possible side effects of XULTOPHY 100/3.6?

XULTOPHY 100/3.6 may cause serious side effects that can lead to death, including:

- See “What is the most important information I should know about XULTOPHY 100/3.6?”
- inflammation of your pancreas (pancreatitis). Stop using XULTOPHY 100/3.6 and call your healthcare provider right away if you have severe pain in your stomach area (abdomen) that will not go away, with or without vomiting. You may feel the pain from your abdomen to your back.
- low blood sugar (hypoglycemia). Your risk for getting low blood sugar may be higher if you use XULTOPHY 100/3.6 with another medicine that can cause low blood sugar.

Signs and symptoms of low blood sugar may include:

- dizziness or light-headedness
- sweating
- confusion or drowsiness
- headache
- blurred vision
- slurred speech
- shakiness
- fast heartbeat
- anxiety, irritability, or mood changes
- hunger
- weakness
- feeling jittery
- kidney problems (kidney failure). Worsening of kidney failure and sudden kidney failure have happened in people with kidney problems and in people without kidney problems, who have taken liraglutide, one of the ingredients in XULTOPHY 100/3.6. Diarrhea, nausea, and vomiting may cause a loss of fluids (dehydration) which may cause kidney problems to get worse. Tell your healthcare provider if you have diarrhea, nausea, or vomiting. Drink plenty of fluids to help reduce your risk of dehydration during treatment with XULTOPHY 100/3.6.
- serious allergic reactions. Stop using XULTOPHY 100/3.6 and get medical help right away, if you have any symptoms of a serious allergic reaction including:
- hives
- rash
- itching
- fast heartbeat
- fainting or feeling dizzy
- swelling of your face, lips, tongue, or throat
- problems breathing or swallowing
- sudden coughing
- chest pain or tightness
- gallbladder problems. Gallbladder problems have happened in some people who take XULTOPHY 100/3.6. Tell your healthcare provider right away if you get symptoms of gallbladder problems which may include:
- pain in your upper stomach (abdomen)
- fever
- yellowing of skin or eyes (jaundice)
- clay-colored stools
- low potassium in your blood (hypokalemia).
- heart failure. Taking certain diabetes pills called thiazolidinediones or TZDs with XULTOPHY 100/3.6 may cause heart failure in some people. This can happen even if you have never had heart failure or heart problems before. If you already have heart failure, it may get worse while you take TZDs with XULTOPHY 100/3.6. Your healthcare provider should monitor you closely while you are taking TZDs with XULTOPHY 100/3.6. Tell your healthcare provider if you have any new or worse symptoms of heart failure including shortness of breath, tiredness, swelling of your ankles or feet and sudden weight gain. Treatment with TZDs and XULTOPHY 100/3.6 may need to be adjusted or stopped by your healthcare provider if you have new or worse heart failure.
- food or liquid getting into the lungs during surgery or other procedures that use anesthesia or deep sleepiness (deep sedation). XULTOPHY 100/3.6 may increase the chance of food getting into your lungs during surgery or other procedures. Tell all your healthcare providers that you are taking XULTOPHY 100/3.6 before you are scheduled to have surgery or other procedures.

The most common side effects of XULTOPHY 100/3.6 include stuffy or runny nose, sore throat, headache, nausea, diarrhea, increased blood levels of lipase, and upper respiratory tract infection. Talk to your healthcare provider about any side effect that bothers you or does not go away.

These are not all the possible side effects of XULTOPHY 100/3.6.

Call your doctor for medical advice about side effects. You may report side effects to FDA at 1-800-FDA-1088.

Keep XULTOPHY 100/3.6 and all medicines out of the reach of children.

General information about the safe and effective use of XULTOPHY 100/3.6.

Medicines are sometimes prescribed for purposes other than those listed in a Medication Guide. Do not use XULTOPHY 100/3.6 for a condition for which it was not prescribed. Do not give XULTOPHY 100/3.6 to other people, even if they have the same symptoms that you have. It may harm them.

You can ask your pharmacist or healthcare provider for information about XULTOPHY 100/3.6 that is written for health professionals.

What are the ingredients in XULTOPHY 100/3.6?

Active Ingredients: insulin degludec and liraglutide

Inactive Ingredients: glycerol, phenol, zinc, and Water for Injection. Hydrochloric acid or sodium hydroxide may be added to adjust pH.

Manufactured by:

Novo Nordisk Inc.
Plainsboro, NJ 08536

U.S. License Number 1261

For more information, go to www.novonordisk-us.com or call 1-800-727-6500 (Se habla español).

This Medication Guide has been approved by the U.S. Food and Drug Administration.

Revised: 11/2024

Instructions for Use

XULTOPHY® 100/3.6 (ZUL-to-fye)

(insulin degludec and liraglutide) injection

- Do not share your XULTOPHY 100/3.6 pen with another person. You may give an infection to them or get an infection from them.
- XULTOPHY 100/3.6 pen (“pen”) is a prefilled disposable, single-patient-use pen containing 300 units of insulin degludec and 10.8 mg of liraglutide (insulin degludec and liraglutide) injection. You can inject doses from 10 to 50 units in a single injection (with each unit of insulin degludec, the pen also delivers 0.036 mg of liraglutide). The dose can be increased by 1 unit at a time. The dose equals the number of units shown in the dose counter.
- People who are blind or have vision problems should not use the pen without help from a person trained to use the pen.

Supplies you will need to give your XULTOPHY 100/3.6 injection:

• XULTOPHY 100/3.6 pen

• a new NovoFine or NovoTwist needle

• alcohol swab

• a sharps container for throwing away used pens and needles. See “After your injection” at the end of these instructions.

Preparing your XULTOPHY 100/3.6 pen:

• Wash your hands with soap and water.

• Before you start to prepare your injection, check the XULTOPHY 100/3.6 pen label before each use to make sure it is your XULTOPHY 100/3.6 pen.

• XULTOPHY 100/3.6 should look clear and colorless. Do not use XULTOPHY 100/3.6 if it is cloudy or colored.

• Do not use XULTOPHY 100/3.6 past the expiration date printed on the label or 21 days after you start using the pen.

• Always use a new needle for each injection to help ensure sterility and prevent blocked needles. Do not reuse or share needles with another person. You may give other people a serious infection or get a serious infection from them.

Step 1:

• Pull pen cap straight off (See Figure B).

Step 2:

• Check the liquid in the pen (See Figure C). XULTOPHY 100/3.6 should look clear and colorless. Do not use it if it looks cloudy or colored.

Step 3:

• Select a new needle.

• Pull off the paper tab from the outer needle cap (See Figure D).

Step 4:

• Push the capped needle straight onto the pen and twist the needle on until it is tight (See Figure E).

Step 5:

• Pull off the outer needle cap. Do not throw it away (See Figure F).

Step 6:

• Pull off the inner needle cap and throw it away (See Figure G).

Priming your XULTOPHY 100/3.6 pen:

Step 7:

• Turn the dose selector to select the priming symbol (). (See Figure H).

Step 8:

• Hold the pen with the needle pointing up. Tap the top of the pen gently a few times to let any air bubbles rise to the top (See Figure I).

Step 9:

• Hold the pen with the needle pointing up. Press and hold in the dose button until the dose counter shows “0”. The “0” must line up with the dose pointer.

• A drop of XULTOPHY 100/3.6 should be seen at the needle tip (See Figure J).

- If you do not see a drop of XULTOPHY 100/3.6, repeat steps 7 to 9, no more than 6 times, until a drop of XULTOPHY 100/3.6 appears at the needle tip.
- If you still do not see a drop of XULTOPHY 100/3.6, change the needle and repeat steps 7 to 9.

Selecting your dose: Make sure you prime your pen before setting your dose.

Step 10:

XULTOPHY 100/3.6 pen is made to deliver the number of units that your healthcare provider prescribed. Take your dose exactly as your healthcare provider tells you to. Do not change your dosing schedule without first talking to your healthcare provider.

• Turn the dose selector to select the dose you need to inject. The dose pointer should line up with your dose (See Figure K).

- If you select the wrong dose, you can turn the dose selector forwards or backwards to the correct dose.
- The even numbers are printed on the dial.
- The odd numbers are shown as lines.

• The XULTOPHY 100/3.6 pen scale will show you how much XULTOPHY 100/3.6 is left in your pen (See Figure L).

• To see how much XULTOPHY 100/3.6 is left in your pen:

- Turn the dose selector until it stops. The dose counter will line up with the dose that is left in your pen. If the dose counter shows 50, there is a dose of at least 50 units left in your pen.
- If the dose counter shows between 10 and 50, the number shown in the dose counter is the total units left in your pen.
- If there is not enough XULTOPHY 100/3.6 left in your pen for a full dose, do not use it. Use a new XULTOPHY 100/3.6 pen.

Giving your injection:

• Inject your XULTOPHY 100/3.6 exactly as your healthcare provider has shown you. Your healthcare provider should tell you if you need to pinch the skin before injecting.

• XULTOPHY 100/3.6 can be injected under the skin (subcutaneously) of your stomach area (abdomen), upper legs (thighs) or upper arms.

• Change (rotate) your injection sites within the area you choose for each dose to reduce your risk of getting lipodystrophy (pits in skin or thickened skin) and localized cutaneous amyloidosis (skin with lumps) at the injection sites. Do not use the same injection site for each injection. Do not inject where the skin has pits, is thickened, or has lumps. Do not inject where the skin is tender, bruised, scaly or hard, or into scars or damaged skin.

Step 11:

• Choose your injection site (stomach, upper legs or upper arms) and wipe the skin with an alcohol swab (See Figure M). Let the injection site dry before you inject your dose.

Step 12:

• Insert the needle into your skin (See Figure N).

- Make sure you can see the dose counter. Do not cover it with your fingers, this can stop your injection.

Step 13:

• Press and hold down the dose button until the dose counter shows “0” (See Figure O).

- The “0” must line up with the dose pointer. You may hear or feel a click.

Step 14:

• Keep the needle in your skin after the dose counter has returned to “0” and slowly count to 6 (See Figure P).

- When the dose counter returns to “0”, you will not get your full dose until 6 seconds later.
- If the needle is removed before you count to 6, you may see a stream of XULTOPHY 100/3.6 coming from the needle tip.
- If you see a stream of XULTOPHY 100/3.6 coming from the needle tip you will not get your full dose. If this happens you should check your blood sugar levels more often because you may need more XULTOPHY 100/3.6.

Step 15:

• Pull the needle out of your skin (See Figure Q).

- If you see blood after you take the needle out of your skin, press the injection site lightly with a piece of gauze or an alcohol swab. Do not rub the area.

Step 16:

• Carefully remove the needle from the pen after each use and throw it away (See Figure R).

- Do not recap the needle. Recapping the needle can lead to needle stick injury.

Note: If you do not have a sharps container, follow the steps below:

- Carefully slip the needle into the outer needle cap (See Figure S). Safely remove the needle and throw it away as soon as you can.
- Do not store the pen with the needle attached. Storing without the needle attached helps prevent leaking, blocking of the needle, and air from entering the pen.

Step 17:

• Replace the pen cap by pushing it straight on (See Figure T).

After your injection:

• The used XULTOPHY pen may be thrown away in your household trash after you have removed the needle.

• Put your used needles in a FDA-cleared sharps disposal container right away after use. Do not throw away (dispose of) loose needles in your household trash.

• If you do not have a FDA-cleared sharps disposal container, you may use a household container that is:

- made of a heavy-duty plastic
- can be closed with a tight-fitting, puncture resistant lid, without sharps being able to come out
- upright and stable during use
- leak-resistant
- properly labeled to warn of hazardous waste inside the container

• When your sharps disposal container is almost full, you will need to follow your community guidelines for the right way to dispose of your sharps disposal container. There may be state or local laws about how you should throw away used needles and syringes. For more information about the safe sharps disposal, and for specific information about sharps disposal in the state that you live in, go to the FDA’s website at: http://www.fda.gov/safesharpsdisposal.

• Do not dispose of your used sharps disposal container in your household trash unless your community guidelines permit this. Do not recycle your used sharps disposal container.

How should I store my XULTOPHY 100/3.6 pen?

Before use:

• Store unused XULTOPHY 100/3.6 pens in the refrigerator at 36°F to 46°F (2°C to 8°C).

• Do not freeze XULTOPHY 100/3.6. Do not use XULTOPHY 100/3.6 if it has been frozen.

• Unused pens may be used until the expiration date printed on the label, if kept in the refrigerator.

• If XULTOPHY 100/3.6 is stored outside of refrigeration prior to first use, it should be used or thrown away within 21 days.

• Store the pens in the carton they come in to keep them clean and protected from light.

Pen in use:

• Store the pen you are currently using at room temperature at 59°F to 86°F (15°C to 30°C) or in a refrigerator at 36°F to 46°F (2°C to 8°C).

• Do not freeze XULTOPHY 100/3.6. Do not use XULTOPHY 100/3.6 if it has been frozen.

• Keep XULTOPHY 100/3.6 away from heat and light.

• The XULTOPHY 100/3.6 pen you are using should be thrown away after 21 days, even if it still has XULTOPHY 100/3.6 left in it and the expiration date has not passed.

General Information about the safe and effective use of XULTOPHY 100/3.6.

• Keep XULTOPHY 100/3.6 pens and needles out of the reach of children.

• Always use a new needle for each injection.

This Instructions for Use has been approved by the U.S. Food and Drug Administration.

Manufactured by:

Novo Nordisk Inc.

800 Scudders Mill Road

Plainsboro, New Jersey 08536

U.S. License Number 1261

For more information call Novo Nordisk at 1-800-727-6500

Revised: 06/2022

© 2016 – 2022 Novo Nordisk

PACKAGE/LABEL PRINCIPAL DISPLAY PANEL

Xultophy® 100/3.6

NDC 0169-2911-15

List: 291115

(insulin degludec and liraglutide) injection

For Single Patient Use Only

100 units/mL and 3.6 mg/mL

With each unit of insulin degludec, the pen

also delivers 0.036 mg of liraglutide

5x3 mL Prefilled Pens

For subcutaneous use only

Recommended for use with NovoFine®,

Novofine® Plus or NovoTwist® disposable needles.

Must be refrigerated until first use.

Store at 36°F – 46°F (2°C – 8°C).

Do not freeze.

Protect from light.

Rx Only

Dispense in this sealed carton.

ATTENTION: Dispense the enclosed Medication Guide to each patient.